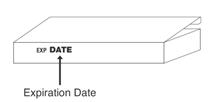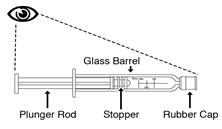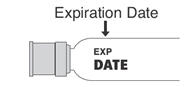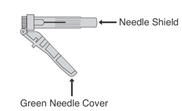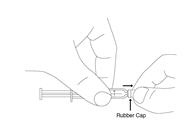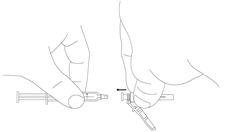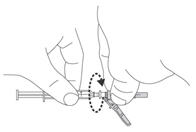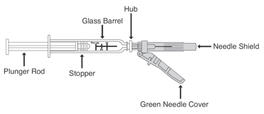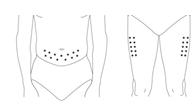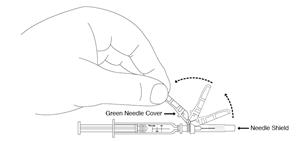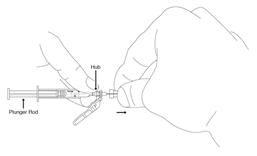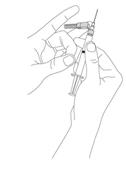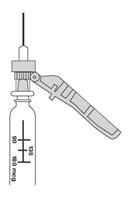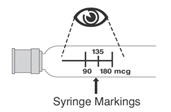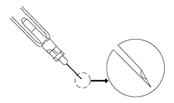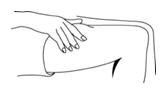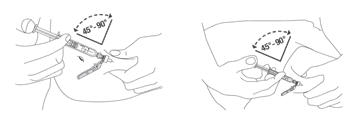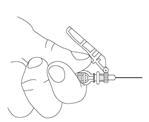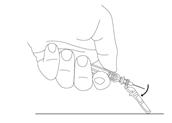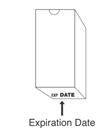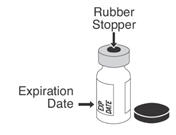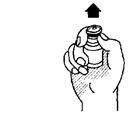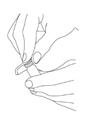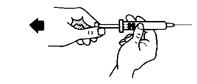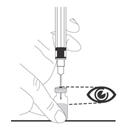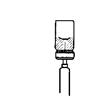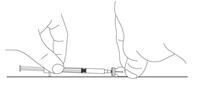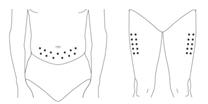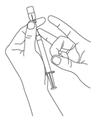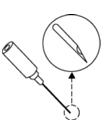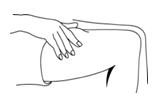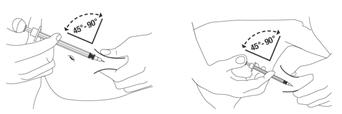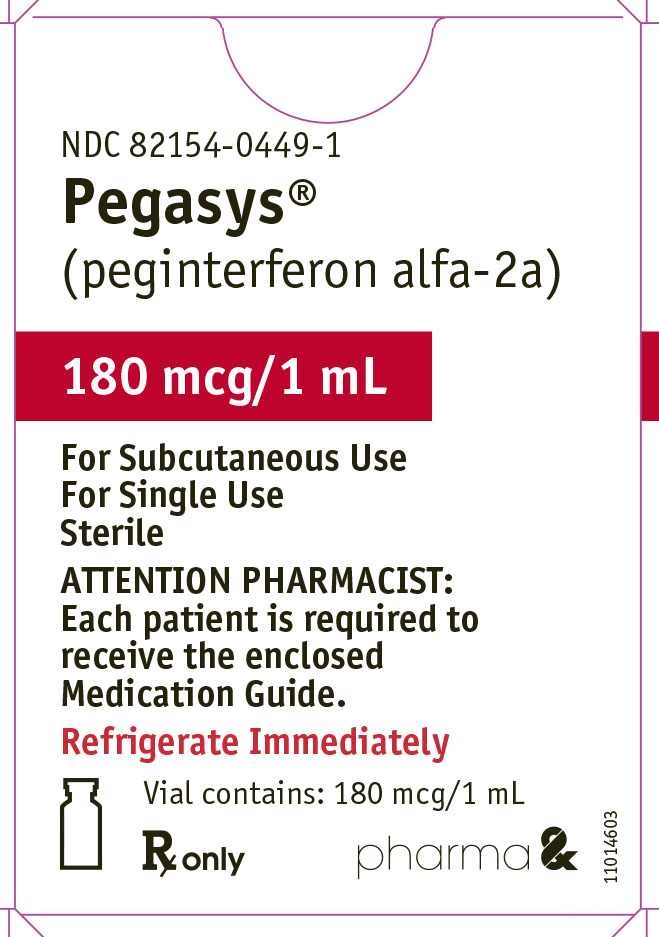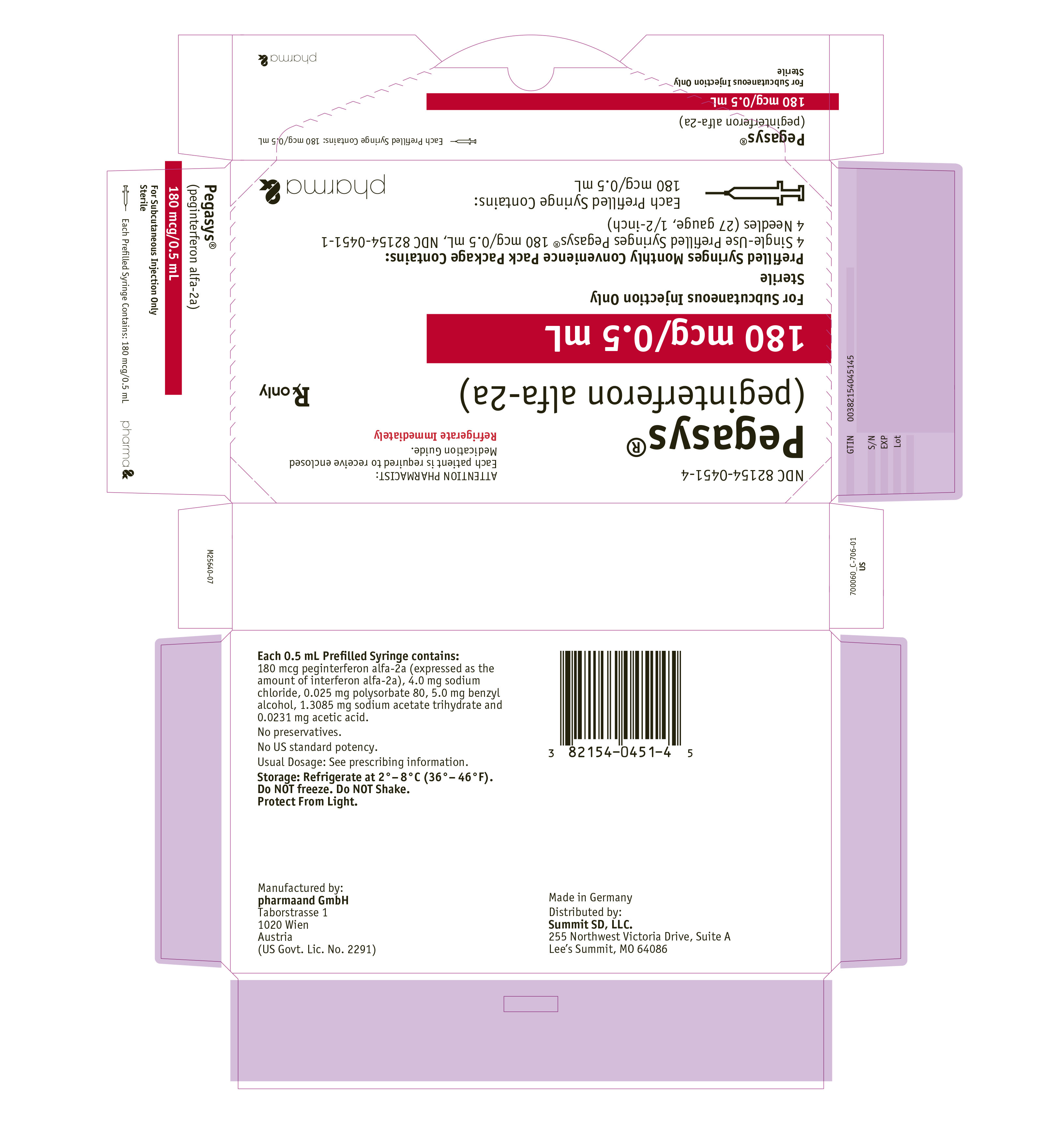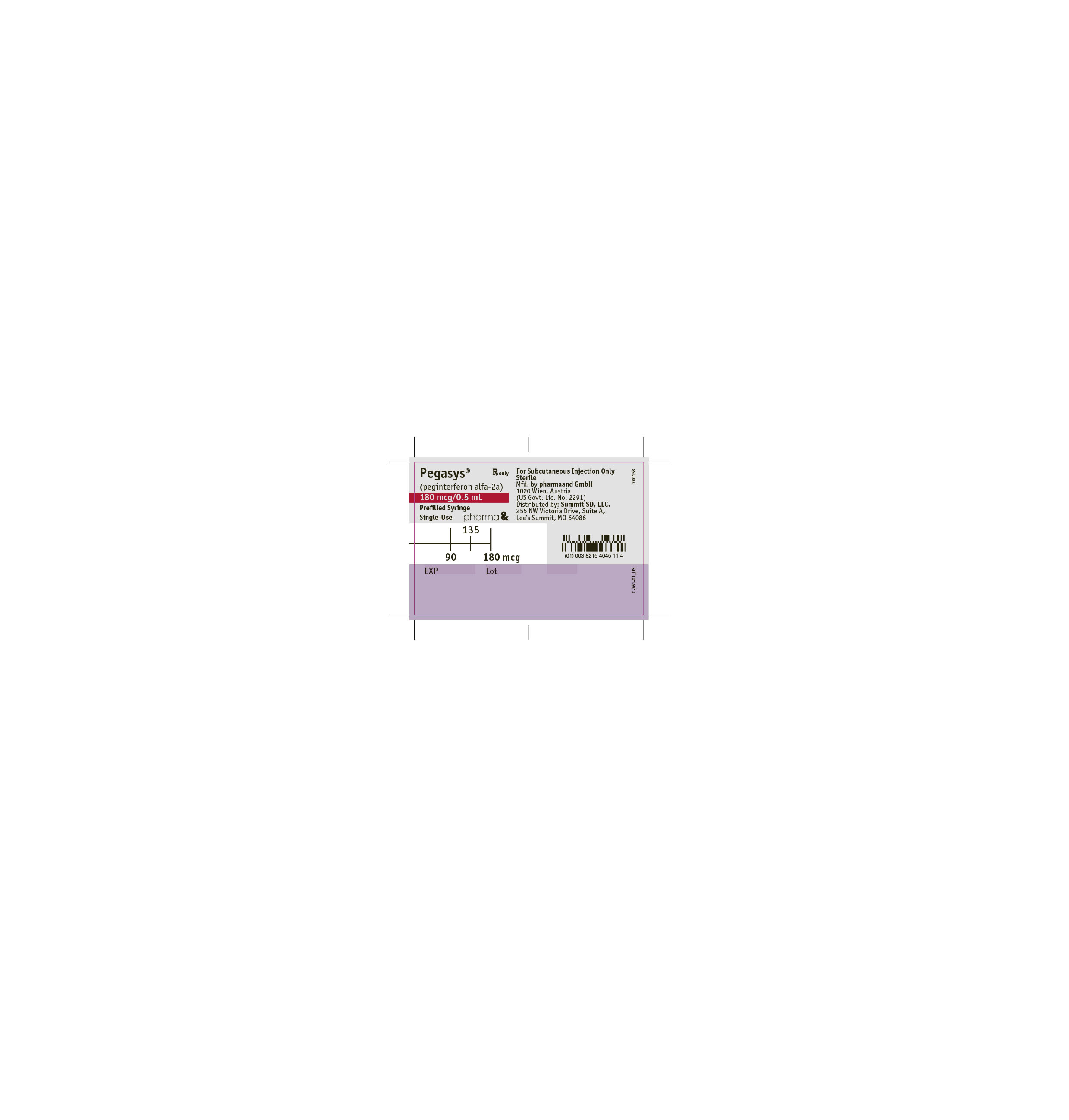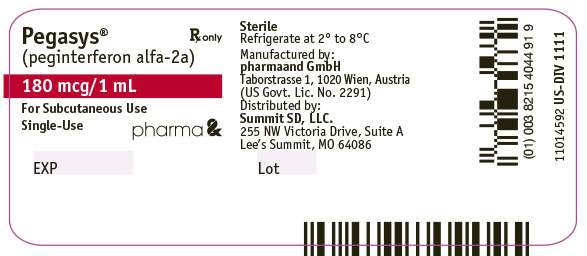 DRUG LABEL: Pegasys
NDC: 82154-0449 | Form: INJECTION, SOLUTION
Manufacturer: pharmaand GmbH
Category: prescription | Type: HUMAN PRESCRIPTION DRUG LABEL
Date: 20250811

ACTIVE INGREDIENTS: PEGINTERFERON ALFA-2A 180 ug/1 mL
INACTIVE INGREDIENTS: POLYSORBATE 80; BENZYL ALCOHOL; ACETIC ACID; SODIUM ACETATE; SODIUM CHLORIDE; WATER

HIGHLIGHTS OF PRESCRIBING INFORMATION

These highlights do not include all the information needed to use PEGASYS safely and effectively. See full prescribing information for PEGASYS.
PEGASYS® (peginterferon alfa-2a) injection, for subcutaneous use
Initial U.S. Approval: 2002

WARNING: RISK OF SERIOUS DISORDERS

See full prescribing information for complete boxed warning.

Risk of Serious Disorders

- May cause or aggravate fatal or life-threatening neuropsychiatric, autoimmune, ischemic, and infectious disorders. Monitor closely and withdraw therapy with persistently severe or worsening signs or symptoms of the above disorders (5)

RECENT MAJOR CHANGES

Warnings and Precautions,; Impact on Growth in Pediatric Patients (5.15) | 12/2023

1 INDICATIONS AND USAGE

PEGASYS is an inducer of the innate immune response indicated for the treatment of

Chronic Hepatitis C (CHC) (1.1)

- Adult Patients: In combination therapy with other hepatitis C virus drugs for adults with compensated liver disease. PEGASYS monotherapy is indicated only if patient has contraindication or significant intolerance to other HCV drugs.
- Pediatric Patients: In combination with ribavirin for pediatric patients 5 years of age and older with compensated liver disease

Chronic Hepatitis B (CHB) (1.2)

- Adult Patients: Treatment of adults with HBeAg-positive and HBeAg-negative chronic hepatitis B (CHB) infection who have compensated liver disease and evidence of viral replication and liver inflammation
- Pediatric Patients: Treatment of non-cirrhotic pediatric patients 3 years of age and older with HBeAg-positive CHB and evidence of viral replication and elevations in serum alanine aminotransferase (ALT)

2 DOSAGE AND ADMINISTRATION

- PEGASYS is administered by subcutaneous injection (2)
- In adult patients with CHC, PEGASYS is dosed as 180 mcg per week and the duration of treatment depends on indication, genotype, and whether it is administered with other HCV antiviral drugs (2.2).
- In adult patients with CHB, PEGASYS is dosed as 180 mcg per week for 48 weeks (2.4).
- In pediatric patients with CHC, PEGASYS is dosed as 180 mcg/1.73 m^2× BSA per week, in combination with ribavirin, and the duration of treatment depends on genotype (2.3)
- In pediatric patients with CHB, PEGASYS is dosed as 180 mcg/1.73 m^2× BSA per week for 48 weeks (2.5):
- Dosage modification is recommended in patients experiencing certain laboratory abnormalities, adverse reactions or renal impairment (2.6, 12.3)

3 DOSAGE FORMS AND STRENGTHS

Injection:

- 180 mcg/mL solution in a single-dose vial (3)
- 180 mcg/0.5 mL solution in a single-dose prefilled syringe (3)

4 CONTRAINDICATIONS

- Autoimmune hepatitis (4)
- Hepatic decompensation in patients with cirrhosis (4)
- Use in neonates/infants (4)
- Known hypersensitivity reactions such as urticaria, angioedema, bronchoconstriction and anaphylaxis to alpha interferons or any component of the product (4)

Additional contraindications for use with other HCV antiviral drugs:

- When used in combination with other HCV antiviral drugs, all contraindications also apply to PEGASYS combination therapy (4)
- Ribavirin is contraindicated in pregnant women and men whose female partners are pregnant (4, 8.1)

5 WARNINGS AND PRECAUTIONS

Use with ribavirin

- Birth defects and fetal death: patients must have a negative pregnancy test prior to therapy, use 2 forms of effective contraception, and have monthly pregnancy tests (5.1)

PEGASYS Clinically Significant Adverse Reactions or Risks

Patients exhibiting the following events should be closely monitored and may require dose reduction or discontinuation of therapy:

- Neuropsychiatric reactions (5.2)
- Cardiovascular disorders (5.3)
- Bone marrow suppression (5.4)
- Autoimmune and endocrine disorders (including thyroid disorders; hyperglycemia) (5.5, 5.6)
- Ophthalmologic disorders (5.7)
- Cerebrovascular disorders (5.8)
- Hepatic decompensation in cirrhotic patients. Exacerbation of hepatitis during hepatitis B treatment (5.9)
- Pulmonary disorders (5.10)
- Infections (bacterial, viral, fungal) (5.11)
- Colitis and pancreatitis (5.12, 5.13)
- Hypersensitivity and serious skin reactions including Stevens-Johnson syndrome (5.14)
- Growth impairment with combination therapy in pediatric patients (5.15)
- Peripheral neuropathy when used in combination with telbivudine (5.16)

6 ADVERSE REACTIONS

- Adult subjects: The most common adverse reactions (incidence greater than 40%) are fatigue/asthenia, pyrexia, myalgia, and headache (6.1)
- Pediatric subjects: The most common adverse reactions are similar to those seen in adults (6.1)

To report SUSPECTED ADVERSE REACTIONS, contact pharma& agent at 1-888-814-7734 or FDA at 1-800-FDA-1088 or www.fda.gov/medwatch.

7 DRUG INTERACTIONS

- Drugs metabolized by CYP1A2: monitor for increased serum levels of theophylline and adjust dose accordingly (7.2)
- Methadone: monitor for signs and symptoms of methadone toxicity (7.3)
- Nucleoside analogues: closely monitor for toxicities. Reduce or discontinue the dose of PEGASYS or ribavirin or both should the events worsen (7.4)
- Zidovudine: monitor for worsening neutropenia and/or anemia with PEGASYS and/or ribavirin (7.4)

8 USE IN SPECIFIC POPULATIONS

- Pediatric patients: Safety and efficacy in CHC pediatric patients less than 5 years old and CHB pediatric patients less than 3 years old have not been established (8.4)
- Geriatric patients: Neuropsychiatric, cardiac, and systemic (flu-like) adverse reactions may be more severe (8.5)
- Patients with hepatic impairment: Clinical status and hepatic function should be closely monitored and treatment should be immediately discontinued if decompensation occurs (8.6)
- Patients with renal impairment: PEGASYS dose should be reduced in patients with creatinine clearance less than 30 mL/min (2.6, 8.7)
- CHB: Safety and efficacy have not been established in hepatitis B patients coinfected with HCV or HIV (8.9)

FULL PRESCRIBING INFORMATION

WARNING: RISK OF SERIOUS DISORDERS

Risk of Serious Disorders

Alpha interferons, including PEGASYS (peginterferon alfa-2a), may cause or aggravate fatal or life-threatening neuropsychiatric, autoimmune, ischemic, and infectious disorders. Patients should be monitored closely with periodic clinical and laboratory evaluations. Therapy should be withdrawn in patients with persistently severe or worsening signs or symptoms of these conditions. In many, but not all cases, these disorders resolve after stopping PEGASYS therapy [see Warnings and Precautions (5.2, 5.5, 5.8, 5.11, 5.14, 5.16), Adverse Reactions (6.1)and Nonclinical Toxicology (13.1)] .

1 INDICATIONS AND USAGE

1.1 Chronic Hepatitis C (CHC)

Adult Patients:PEGASYS, as part of a combination regimen with other hepatitis C virus (HCV) antiviral drugs, is indicated for the treatment of adults with CHC and compensated liver disease. For information about the safe and effective use of other HCV antiviral drugs to be used in combination with PEGASYS, refer to their prescribing information. PEGASYS monotherapy is only indicated for the treatment of patients with CHC and compensated liver disease if there are contraindications or significant intolerance to other HCV antiviral drugs.

Pediatric Patients:PEGASYS in combination with ribavirin is indicated for the treatment of pediatric patients 5 years of age and older with CHC and compensated liver disease.

Limitations of Use:

- PEGASYS alone or in combination with ribavirin without additional HCV antiviral drugs is not recommended for treatment of patients with CHC who previously failed therapy with an interferon-alfa.
- PEGASYS is not recommended for treatment of patients with CHC who have had solid organ transplantation [see Use in Specific Populations (8.8)] .

1.2 Chronic Hepatitis B (CHB)

Adult Patients:PEGASYS is indicated for the treatment of adults with HBeAg-positive and HBeAg-negative CHB infection who have compensated liver disease and evidence of viral replication and liver inflammation.

Pediatric Patients:PEGASYS is indicated for the treatment of HBeAg-positive CHB in non-cirrhotic pediatric patients 3 years of age and older with evidence of viral replication and elevations in serum alanine aminotransferase (ALT).

2 DOSAGE AND ADMINISTRATION

2.1 Dosage Overview

Administer PEGASYS by subcutaneous injection once weekly in the abdomen or thigh for the treatment of:

- Adult patients with CHC without or with HIV coinfection [see Dosage and Administration (2.2)];
- Pediatric patients with CHC [see Dosage and Administration (2.3)] ;
- Adult patients with CHB [see Dosage and Administration (2.4)] ; and
- Pediatric patients with CHB [see Dosage and Administration (2.5)].

For treatment of CHC, use PEGASYS in combination with other HCV antiviral drugs. For information about the recommended dosage and administration and the safe and effective use of these other HCV antiviral drugs, refer to their prescribing information. PEGASYS monotherapy is only indicated in the treatment of CHC if there are contraindications to or significant intolerance to other HCV antiviral drugs.

For dosage modifications in patients with CHC or CHB:

- Due to neutropenia, thrombocytopenia, ALT elevation, and depression [see Dosage and Administration (2.6)] .
- In patients with severe renal impairment (creatinine clearance less than 30 mL/minute) and in patients with creatinine clearance between 30 and 50 mL/minute [see Dosage and Administration (2.6)] .

For important administration instructions for all the PEGASYS injection presentations (i.e., vial and prefilled syringe) [see Dosage and Administration (2.7)].

2.2 Recommended Dosage for Adults with CHC

Dosage in Adults with CHC without HIV Coinfection

Table 1 displays the recommended dosage and duration of PEGASYS and other HCV antiviral drugs in adults with CHC (without HIV coinfection) based on HCV genotype.

For treatment of HCV genotype 1 with PEGASYS in combination with ribavirin or alone, discontinuation of treatment is recommended if at least a 2 log10reduction from baseline in HCV RNA has not been demonstrated by 12 weeks of therapy or if undetectable HCV RNA has not been achieved after 24 weeks of therapy [see Clinical Studies (14)] . Refer to the prescribing information for specific HCV antiviral drugs used in combination with PEGASYS for information on stopping therapy based on treatment response.

Immediately discontinue PEGASYS for hepatic decompensation (Child-Pugh score greater than 6 [class B and C]).

Table 1 Recommended Dosage for PEGASYS for Adults with CHC Infection [If PEGASYS is used in combination with other antiviral drugs for CHC, refer to the prescribing information of the other HCV antiviral drugs for the recommended dosage of the other HCV antiviral drugs and duration of the entire treatment regimen.]
Hepatitis C Virus Genotype | PEGASYS Dosage | PEGASYS Duration
Genotypes 1, 4 [If PEGASYS and ribavirin are used without other HCV antiviral drugs the recommended duration of therapy is 48 weeks.] | 180 mcg subcutaneous injection in thigh or abdomen once weekly | Refer to the prescribing information of HCV antiviral drugs.
Genotypes 2, 3 [If PEGASYS and ribavirin are used without other HCV antiviral drugs the recommended duration of therapy is 24 weeks.] | 180 mcg subcutaneous injection in thigh or abdomen once weekly | Refer to the prescribing information of HCV antiviral drugs.
Genotypes 5, 6 | There are insufficient data for dosage recommendations

If PEGASYS monotherapy is used for treatment of CHC, the recommended PEGASYS dosage is 180 mcg via subcutaneous injection in thigh or abdomen once weekly for 48 weeks.

Dosage in Adults with CHC with HIV Coinfection

The recommended PEGASYS dosage in adults with CHC and HIV coinfection is 180 mcg subcutaneously once weekly in the thigh or abdomen. If PEGASYS is used in combination with other antiviral drugs, refer to the prescribing information of the other HCV antiviral drugs for the recommended dosage of the other HCV antiviral drugs and duration of the entire treatment regimen (including PEGASYS). If PEGASYS and ribavirin are used without other HCV antiviral drugs, the recommended duration of therapy is 48 weeks (regardless of HCV genotype).

2.3 Recommended Dosage for Pediatric Patients with CHC

PEGASYS is administered as 180 mcg/1.73 m^2× BSA subcutaneously once weekly, to a maximum dose of 180 mcg, and should be given in combination with ribavirin. The recommended treatment duration for pediatric patients with HCV genotype 2 or 3 is 24 weeks and for other HCV genotypes is 48 weeks. Patients who initiate treatment prior to their 18thbirthday should maintain the recommended pediatric dosage (not the adult dosage) through the completion of therapy. Refer to the prescribing information of ribavirin for the recommended dosage and duration.

2.4 Recommended Dosage for Adults with CHB

The recommended PEGASYS dosage in adults with CHB is 180 mcg subcutaneously once weekly in the thigh or abdomen for 48 weeks.

2.5 Recommended Dosage for Pediatrics Patients with CHB

The recommended PEGASYS dosage in pediatric patients for HBeAg-positive CHB is 180 mcg/1.73 m^2× BSA subcutaneously once weekly to a maximum dose of 180 mcg. The recommended duration of therapy is 48 weeks.

Maintain the recommended pediatric dosage through the entire duration of therapy in patients who turn 18 years of age during therapy.

2.6 Dosage Modifications

PEGASYS Dosage Modifications Due to Adverse Reactions, Neutropenia or Thrombocytopenia in Adults

Table 2displays the recommended PEGASYS dosage modifications due to adverse reactions, or due to neutropenia, or thrombocytopenia in adults. Following improvement of the adverse reaction, neutropenia or thrombocytopenia, consider re-escalation of the dosage back to the previous dosage [see Warnings and Precautions (5)and Adverse Reactions (6)].

Table 2 Recommended PEGASYS Dosage Modifications in Adults Due to Adverse Reactions, Neutropenia or Thrombocytopenia
Laboratory Values | Recommended PEGASYS Dosage
Neutropenia
ANC 500 to less than 750 cells/mm^3 | Reduce to 135 mcg subcutaneously once weekly
ANC less than 500 cells/mm^3 | Discontinue treatment until ANC values return to more than 1000 cells/mm^3. Reinstitute at 90 mcg subcutaneously once weekly and monitor ANC.
Thrombocytopenia
Platelet 25,000 to less than 50,000 cells/mm^3 | Reduce to 90 mcg subcutaneously once weekly
Platelet less than 25,000 cells/mm^3 | Discontinue treatment
ANC = absolute neutrophil count

PEGASYS Dosage Modifications Due to ALT Elevation in Adults

If ALT increases are progressive despite dose reduction or accompanied by increased bilirubin or evidence of hepatic decompensation, therapy should be immediately discontinued. In CHC patients with progressive ALT increases above baseline values, the dosage of PEGASYS should be reduced to 135 mcg and more frequent monitoring of liver function should be performed. After PEGASYS dosage reduction or withholding, therapy can be resumed after ALT flares subside.

In CHB patients with elevations in ALT (greater than 5 × ULN), more frequent monitoring of liver function should be performed and consideration should be given to either reducing the dosage of PEGASYS to 135 mcg or temporarily discontinuing treatment. After PEGASYS dosage reduction or withholding, therapy can be resumed after ALT flares subside.

In adult patients with persistent, severe (ALT greater than 10 times above the upper limit of normal) hepatitis B flares, consideration should be given to discontinuation of treatment.

PEGASYS Dosage Modifications Due to Depression in Adults and in Pediatric Patients

Table 3 displays the recommended PEGASYS dosage modifications in adult and pediatric patients who develop interferon-related depression or whose underlying depression worsens. Table 3 also includes recommended frequency of psychiatric visits.

Table 3 Recommended PEGASYS Dosage Modifications and Psychiatric Visits Due to Depression in Adult & Pediatric Patients
Depression Severity | Initial Depression Management (4-8 weeks) |  | Depression Management After 8 Weeks
Depression Severity | Dosage Modification | Visit Schedule | Depression Severity Remains Stable | Depression Severity Improves | Depression Severity Worsens
Mild | No change | Evaluate once weekly by visit and/or phone | Continue weekly visit schedule | Resume normal visit schedule | Consider psychiatric consultation. Discontinue PEGASYS or reduce dosage to 135 mcg in adults (135 mcg/1.73 m^2× BSA for pediatric patients) or 90 mcg once weekly for adults (90 mcg/1.73 m^2× BSA for pediatric patients)
Moderate | Decrease PEGASYS dosage to 135 mcg in adults (135 mcg/1.73 m^2× BSA for pediatric patients) or 90 mcg in adults (90 mcg/1.73 m^2× BSA for pediatric patients) once weekly | Evaluate once weekly (office visit at least every other week) | Consider psychiatric consultation. Continue reduced dosing | If symptoms improve and are stable for 4 weeks, may resume normal visit schedule. Continue reduced dosage or return to normal dosage | Obtain immediate psychiatric consultation; Discontinue PEGASYS permanently.
Severe | Discontinue PEGASYS permanently | Obtain immediate psychiatric consultation | Psychiatric therapy necessary

PEGASYS Dosage Modifications Due to Adverse Reactions or Laboratory Abnormalities in Pediatric Patients

Table 4 displays the recommended PEGASYS dosage modifications due to adverse reactions, neutropenia, thrombocytopenia, or elevated ALT in pediatric patients.

Table 4 Recommended PEGASYS Dosage Modifications for Neutropenia, Thrombocytopenia, and Elevated ALT in Pediatric Patients
 | Laboratory Abnormality | Recommended PEGASYS Dosage Modification
 | Laboratory Abnormality | CHC | CHB
Neutropenia | ANC 750-999 cells/mm^3 | Week 1-2: immediate modification to 135 mcg/1.73 m^2× BSA Week 3-48: no modification. | No dosage modification.
Neutropenia | ANC 500-749 cells/mm^3 | Week 1-2:; - Delay or hold dosage until ANC is more than 750 cells/mm^3then resume dosage at 135 mcg/1.73 m^2× BSA - Assess three times weekly to verify ANC more than 750 cells/mm^3; Week 3-48: immediate modification to 135 mcg/1.73 m^2× BSA. | Immediate modification to 135 mcg/1.73 m^2× BSA.
Neutropenia | ANC 250-499 cells/mm^3 | Week 1-2: Delay or hold dosage until ANC is more than 750 cells/mm^3then resume dose at 90 mcg/1.73 m^2× BSA; Week 3-48: Delay or hold dosage until ANC is more than 750 cells/mm^3then resume dosage at 135 mcg/1.73 m^2× BSA. | Interrupt dosing until ANC is more than or equal to 1000 cells/mm^3, then resume dose with 90 mcg/1.73 m^2× BSA and monitor.
Neutropenia | ANC less than 250 cells/mm^3(or febrile neutropenia): | Discontinue treatment. | Discontinue treatment.
Thrombocytopenia | Platelet 25,000 to less than 50,000 cells/mm^3 | Reduce dosage to 90 mcg/1.73 m^2× BSA. | Reduce dosage to 90 mcg/1.73 m^2× BSA.
Thrombocytopenia | Platelet less than 25,000 cells/mm^3 | Discontinue treatment. | Discontinue treatment.
Increased alanine transaminase (ALT) | For persistent or increasing elevations more than or equal to 5 but less than 10 × ULN | - Modify dosage to 135 mcg/1.73 m^2× BSA. - Monitor weekly, reduce dosage further if necessary, until stable or ALT level decreases. | - Modify dosage to 135 mcg/1.73 m^2× BSA. - Monitor weekly ALT level to ensure it is stable or decreasing
Increased alanine transaminase (ALT) | For persistent ALT values more than or equal to 10 × ULN | Discontinue treatment. | Discontinue treatment.
ANC = absolute neutrophil count

PEGASYS Dosage Modifications for Adults with Renal Impairment

Prior to administering PEGASYS, evaluate renal function. Table 5displays the recommended dosage modifications for adults with creatinine clearance less than 30 mL/minute, including patients with end-stage renal disease requiring hemodialysis [see Use in Specific Populations (8.7)and Clinical Pharmacology (12.3)]. Refer to the respective prescribing information of other HCV antiviral drugs regarding use in patients with renal impairment.

Table 5 PEGASYS Dosage Modification for Adults with Renal Impairment
Creatinine Clearance | Recommended PEGASYS Dosage
30 to 50 mL/minute | 180 mcg once weekly
Less than 30 mL/minute including patients on hemodialysis | 135 mcg once weekly
Less than 30 mL/minute including patients on hemodialysis [If severe adverse reactions or laboratory abnormalities develop, PEGASYS dose can be reduced to 90 mcg once weekly until adverse reactions abate. If intolerance persists after dosage adjustment, PEGASYS should be discontinued.] | 135 mcg once weekly

PEGASYS Dosage Modifications for Pediatric Patients with Renal Impairment:

Dosage recommendations for pediatric patients with renal impairment are not available.

2.7 Preparation and Administration

Preparation and administration in adults:After proper training in subcutaneous injection, a patient may subcutaneously self-inject with PEGASYS if a healthcare provider determines that it is appropriate [see Instructions for Use] . Visually inspect PEGASYS for particulate matter and discoloration before administration (do not use if particulate matter is visible or product is discolored). Use a sterile needle and syringe to withdraw and administer PEGASYS.

Table 6displays the recommended volume of PEGASYS to be administered for the single-dose vial and prefilled syringe presentations for the different dosages recommendations (i.e., 180, 135, or 90 mcg once weekly). Discard the unused portion of PEGASYS in single-use vials or prefilled syringes in excess of the labeled volume.

Table 6 Use of the Vial and Prefilled Syringe for Adult PEGASYS Dosages
Recommended PEGASYS Dosage | PEGASYS Dosage Forms
 | 180 mcg/mL in a vial | 180 mcg/0.5 mL in a prefilled syringe [Syringe marked at 90 mcg, 135 mcg, and 180 mcg graduations]
180 mcg | Use entire 1 mL | Use entire 0.5 mL
135 mcg | Use 0.75 mL | Use 0.375 mL
90 mcg | Use 0.5 mL | Use 0.25 mL

Preparation and administration in pediatric patients: Use the 180 mcg/ml vial to prepare pediatric dose. Use a sterile needle and syringe to withdraw and administer PEGASYS. The recommended volume of PEGASYS for pediatric dosing is based on the dosage (180 mcg/1.73 m^2× BSA). It should be drawn from the 180 mcg/mL vial using a 1 mL tuberculin syringe.

3 DOSAGE FORMS AND STRENGTHS

PEGASYS is a colorless to slightly yellowish solution available as:

- Injection: 180 mcg/mL in a single-dose vial
- Injection: 180 mcg/0.5 mL in a single-dose prefilled syringe

4 CONTRAINDICATIONS

PEGASYS is contraindicated in patients with:

- Known hypersensitivity reactions such as urticaria, angioedema, bronchoconstriction, anaphylaxis, or Stevens-Johnson syndrome to alpha interferons, including PEGASYS, or any of its components.
- Autoimmune hepatitis
- Hepatic decompensation (Child-Pugh score greater than 6 [class B and C]) in cirrhotic patients before treatment
- Hepatic decompensation with Child-Pugh score greater than or equal to 6 in cirrhotic CHC patients coinfected with HIV before treatment

PEGASYS is contraindicated in neonates and infants because it contains benzyl alcohol. Benzyl alcohol is associated with an increased incidence of neurologic and other complications which are sometimes fatal in neonates and infants.

When PEGASYS is used in combination with other HCV antiviral drugs, the contraindications applicable to those agents are applicable to combination therapies. PEGASYS combination treatment with ribavirin is contraindicated in women who are pregnant and men whose female partners are pregnant [See Warnings and Precautions (5.1)and Use in Specific Populations (8.1)].

Refer to the prescribing information of the other HCV antiviral drugs, including ribavirin, for a list of their contraindications.

5 WARNINGS AND PRECAUTIONS

Refer to the prescribing information of the other HCV antiviral drugs, including ribavirin, for their Warnings and Precautions.

5.1 Pregnancy: Use with ribavirin

Ribavirin may cause birth defects and/or death of the exposed fetus.Patients must avoid pregnancy (female patients or female partners of male patients) while taking PEGASYS and ribavirin combination therapy. Ribavirin therapy should not be started unless a confirmed negative pregnancy test has been obtained immediately prior to initiation of therapy. Women of childbearing potential and men must use two forms of effective contraception during treatment and for at least 6 months after treatment has concluded. Routine monthly pregnancy tests must be performed during this time [see Contraindications (4), Patient Counseling Information (17)and ribavirin labeling] .

5.2 Neuropsychiatric Reactions

Life-threatening or fatal neuropsychiatric reactions may manifest in all patients receiving therapy with PEGASYS and include suicide, suicidal ideation, homicidal ideation, depression, relapse of drug addiction, and drug overdose. These reactions may occur in patients with and without previous psychiatric illness.

PEGASYS should be used with extreme caution in all patients who report a history of depression. Neuropsychiatric adverse events observed with alpha interferon treatment include aggressive behavior, psychoses, hallucinations, bipolar disorders, and mania. Physicians should monitor all patients for evidence of depression and other psychiatric symptoms. Patients should be advised to report any sign or symptom of depression or suicidal ideation to their prescribing physicians. In severe cases, therapy should be stopped immediately and psychiatric intervention instituted [see Boxed Warning, Adverse Reactions (6.1)and Dosage and Administration (2.6)] .

5.3 Cardiovascular Disorders

Hypertension, supraventricular arrhythmias, chest pain, and myocardial infarction have been observed in patients treated with PEGASYS. PEGASYS should be administered with caution to patients with pre-existing cardiac disease. Because cardiac disease may be worsened by ribavirin-induced anemia, patients with a history of significant or unstable cardiac disease should not receive PEGASYS/ribavirin [see ribavirin prescribing information].

5.4 Bone Marrow Suppression

PEGASYS suppresses bone marrow function and may result in severe cytopenias. Ribavirin may potentiate the neutropenia and lymphopenia induced by alpha interferons including PEGASYS. Very rarely, alpha interferons may be associated with aplastic anemia. It is advised that complete blood counts (CBC) be obtained pre-treatment and monitored routinely during therapy [see ribavirin prescribing information].

PEGASYS/ribavirin should be used with caution in patients with baseline neutrophil counts less than 1,500 cells/mm^3, with baseline platelet counts less than 90,000 cells/mm^3or baseline hemoglobin less than 10 g/dL. PEGASYS therapy should be discontinued, at least temporarily, in patients who develop severe decreases in neutrophil and/or platelet counts [see Dosage and Administration (2.6)] .

Severe neutropenia and thrombocytopenia occur with a greater incidence in HIV coinfected patients than monoinfected patients and may result in serious infections or bleeding [see Adverse Reactions (6.1)] .

Pancytopenia (marked decreases in RBCs, neutrophils and platelets) and bone marrow suppression have been reported in the literature to occur within 3 to 7 weeks after the concomitant administration of pegylated interferon/ribavirin and azathioprine. In this limited number of patients (n=8), myelotoxicity was reversible within 4 to 6 weeks upon withdrawal of both HCV antiviral therapy and concomitant azathioprine and did not recur upon reintroduction of either treatment alone. PEGASYS, ribavirin, and azathioprine should be discontinued for pancytopenia, and pegylated interferon/ribavirin should not be re-introduced with concomitant azathioprine.

5.5 Autoimmune Disorders

Development or exacerbation of autoimmune disorders including myositis, hepatitis, thrombotic thrombocytopenic purpura, idiopathic thrombocytopenic purpura, psoriasis, rheumatoid arthritis, interstitial nephritis, thyroiditis, and systemic lupus erythematosus have been reported in patients receiving alpha interferon. PEGASYS should be used with caution in patients with autoimmune disorders [see Boxed Warning] .

5.6 Endocrine Disorders

PEGASYS causes or aggravates hypothyroidism and hyperthyroidism. Hyperglycemia, hypoglycemia, and diabetes mellitus have been observed to develop in patients treated with PEGASYS. Patients with these conditions at baseline who cannot be effectively treated by medication should not begin PEGASYS therapy. Patients who develop these conditions during treatment and cannot be controlled with medication may require discontinuation of PEGASYS therapy.

5.7 Ophthalmologic Disorders

Decrease or loss of vision, retinopathy including macular edema, retinal artery or vein thrombosis, retinal hemorrhages and cotton wool spots, optic neuritis, papilledema and serous retinal detachment are induced or aggravated by treatment with PEGASYS or other alpha interferons. All patients should receive an eye examination at baseline. Patients with pre-existing ophthalmologic disorders (e.g., diabetic or hypertensive retinopathy) should receive periodic ophthalmologic exams during interferon alpha treatment. Any patient who develops ocular symptoms should receive a prompt and complete eye examination. PEGASYS treatment should be discontinued in patients who develop new or worsening ophthalmologic disorders.

5.8 Cerebrovascular Disorders

Ischemic and hemorrhagic cerebrovascular events have been observed in patients treated with interferon alfa-based therapies, including PEGASYS. Events occurred in patients with few or no reported risk factors for stroke, including patients less than 45 years of age. Because these are spontaneous reports, estimates of frequency cannot be made and a causal relationship between interferon alfa-based therapies and these events is difficult to establish [see Boxed Warning] .

5.9 Hepatic Failure and Hepatitis Exacerbations

Chronic hepatitis C (CHC) patients with cirrhosis may be at risk of hepatic decompensation and death when treated with alpha interferons, including PEGASYS. Cirrhotic CHC patients coinfected with HIV receiving highly active antiretroviral therapy (HAART) and interferon alfa-2a with or without ribavirin appear to be at increased risk for the development of hepatic decompensation compared to patients not receiving HAART. In Study 7 [see Clinical Studies (14.3)] , among 129 CHC/HIV cirrhotic subjects receiving HAART, 14 (11%) of these subjects across all treatment arms developed hepatic decompensation resulting in 6 deaths. All 14 subjects were on NRTIs, including stavudine, didanosine, abacavir, zidovudine, and lamivudine. These small numbers of patients do not permit discrimination between specific NRTIs for the associated risk. During treatment, patients' clinical status and hepatic function should be closely monitored, and PEGASYS/ribavirin treatment should be immediately discontinued in patients with hepatic decompensation [see Contraindications (4)] .

Exacerbations of hepatitis during hepatitis B therapy are not uncommon and are characterized by transient and potentially severe increases in serum ALT. Chronic hepatitis B subjects experienced transient acute exacerbations (flares) of hepatitis B (ALT elevation greater than 10-fold higher than the upper limit of normal) during PEGASYS treatment (12% and 18%) and post-treatment (7% and 12%) in HBeAg-negative and HBeAg-positive subjects, respectively. Marked transaminase flares while on PEGASYS therapy have been accompanied by other liver test abnormalities. Patients experiencing ALT flares should receive more frequent monitoring of liver function. PEGASYS dose reduction should be considered in patients experiencing transaminase flares. If ALT increases are progressive despite reduction of PEGASYS dose or are accompanied by increased bilirubin or evidence of hepatic decompensation, PEGASYS should be immediately discontinued [see Adverse Reactions (6.1)and Dosage and Administration (2.6)] .

5.10 Pulmonary Disorders

Dyspnea, pulmonary infiltrates, pneumonia, bronchiolitis obliterans, interstitial pneumonitis, pulmonary hypertension and sarcoidosis, some resulting in respiratory failure and/or patient deaths, may be induced or aggravated by PEGASYS or alpha interferon therapy. Recurrence of respiratory failure has been observed with interferon rechallenge. PEGASYS combination treatment should be suspended in patients who develop pulmonary infiltrates or pulmonary function impairment. Patients who resume interferon treatment should be closely monitored.

5.11 Infections

While fever may be associated with the flu-like syndrome reported commonly during interferon therapy, other causes of high or persistent fever must be ruled out, particularly in patients with neutropenia. Serious and severe infections (bacterial, viral, or fungal), some fatal, have been reported during treatment with alpha interferons including PEGASYS. Appropriate anti-infective therapy should be started immediately and discontinuation of therapy should be considered [see Boxed Warning] .

5.12 Colitis

Ulcerative and hemorrhagic/ischemic colitis, sometimes fatal, have been observed within 12 weeks of starting alpha interferon treatment. Abdominal pain, bloody diarrhea, and fever are the typical manifestations of colitis. PEGASYS should be discontinued immediately if these symptoms develop. The colitis usually resolves within 1 to 3 weeks of discontinuation of alpha interferon.

5.13 Pancreatitis

Pancreatitis, sometimes fatal, has occurred during alpha interferon and ribavirin treatment. PEGASYS/ribavirin should be suspended if symptoms or signs suggestive of pancreatitis are observed. PEGASYS/ribavirin should be discontinued in patients diagnosed with pancreatitis.

5.14 Hypersensitivity

Severe acute hypersensitivity reactions (e.g., urticaria, angioedema, bronchoconstriction, and anaphylaxis) have been observed during alpha interferon and ribavirin therapy. If such reaction occurs, therapy with PEGASYS/ribavirin should be discontinued and appropriate medical therapy immediately instituted. Serious skin reactions including vesiculobullous eruptions, reactions in the spectrum of Stevens-Johnson Syndrome (erythema multiforme major) with varying degrees of skin and mucosal involvement and exfoliative dermatitis (erythroderma) have been reported in patients receiving PEGASYS with and without ribavirin. Patients developing signs or symptoms of severe skin reactions must discontinue therapy [see Adverse Reactions (6.2)] .

5.15 Impact on Growth in Pediatric Patients

Growth inhibition was observed in CHC pediatric subjects 5 to 17 years of age during combination therapy for up to 48 weeks with PEGASYS plus ribavirin. At the end of treatment, 43% of subjects were more than 15 percentiles below their baseline weight curve, and 25% of subjects were more than 15 percentiles below their baseline height curve. At the end of 2 years follow-up after treatment, most subjects had returned to baseline normative curve percentiles for weight and height; 16% of subjects were more than 15 percentiles below their baseline weight curve and 11% were more than 15 percentiles below their baseline height curve.

The available longer-term data on subjects who were followed up to 6 years post-treatment are too limited to determine the risk of reduced adult height in some patients [see Clinical Trials Experience (6.1)].

Growth inhibition was also observed in CHB pediatric subjects 3 to 17 years of age during therapy with PEGASYS lasting up to 48 weeks. At Week 48 of treatment 13% of subjects were more than 15 percentiles below their baseline weight curve and 6% were more than 15 percentiles below their baseline height curve. At 24 weeks after the end of treatment, 11% of subjects were more than 15 percentiles below their baseline weight curve and 12% were more than 15 percentiles below their baseline height curve. At 5 years post-treatment the percentage of subjects with decrease of more than 15 percentiles from baseline was 29% for weight and 18% for height. [see Clinical Trials Experience (6.1)].

5.16 Peripheral Neuropathy

Peripheral neuropathy has been reported when alpha interferons were given in combination with telbivudine. In one clinical trial, an increased risk and severity of peripheral neuropathy was observed with the combination use of telbivudine and PEGASYS as compared to telbivudine alone. The safety and efficacy of telbivudine in combination with interferons for the treatment of CHB have not been demonstrated.

5.17 Laboratory Tests

Before beginning PEGASYS or PEGASYS combination therapy, standard hematological and biochemical laboratory tests are recommended for all patients. Pregnancy screening for women of childbearing potential must be performed. Patients who have pre-existing cardiac abnormalities should have electrocardiograms administered before treatment with PEGASYS/ribavirin.

After initiation of therapy, hematological tests should be performed at 2 weeks and 4 weeks and biochemical tests should be performed at 4 weeks. Additional testing should be performed periodically during therapy. In adult clinical studies, the CBC (including hemoglobin level and white blood cell and platelet counts) and chemistries (including liver function tests and uric acid) were measured at 1, 2, 4, 6, and 8 weeks, and then every 4 to 6 weeks or more frequently if abnormalities were found. In a pediatric clinical trial, hematological and chemistry assessments were at 1, 3, 5, and 8 weeks, then every 4 weeks. Thyroid stimulating hormone (TSH) was measured every 12 weeks. Monthly pregnancy testing should be performed during combination therapy and for 6 months after discontinuing therapy.

The entrance criteria used for the clinical studies of PEGASYS may be considered as a guideline to acceptable baseline values for initiation of treatment:

- Platelet count greater than or equal to 90,000 cells/mm^3(as low as 75,000 cells/mm^3in HCV subjects with cirrhosis or 70,000 cells/mm^3in subjects with CHC and HIV)
- Absolute neutrophil count (ANC) greater than or equal to 1,500 cells/mm^3
- Serum creatinine concentration less than 1.5 × upper limit of normal
- TSH and T4within normal limits or adequately controlled thyroid function
- CD4+ cell count greater than or equal to 200 cells/mm^3or CD4+ cell count greater than or equal to 100 cells/mm^3but less than 200 cells/mm^3and HIV-1 RNA less than 5,000 copies/mL in subjects coinfected with HIV
- Hemoglobin greater than or equal to 12 g/dL for women and greater than or equal to 13 g/dL for men in CHC monoinfected subjects
- Hemoglobin greater than or equal to 11 g/dL for women and greater than or equal to 12 g/dL for men in subjects with CHC and HIV

6 ADVERSE REACTIONS

In clinical trials, a broad variety of serious adverse reactions were observed in 1,010 subjects who received PEGASYS at doses of 180 mcg for 48 weeks, alone or in combination with ribavirin [see Boxed Warningand Warnings and Precautions (5)] . The most common life-threatening or fatal events induced or aggravated by PEGASYS and ribavirin include depression, suicide, relapse of drug abuse/overdose, and bacterial infections, each occurring at a frequency of less than 1%. Hepatic decompensation occurred in 2% (10/574) of CHC/HIV subjects [see Warnings and Precautions (5.9)] .

6.1 Clinical Trials Experience

Because clinical trials are conducted under widely varying and controlled conditions, adverse reaction rates observed in clinical trials of a drug cannot be directly compared to rates in the clinical trials of another drug, and may not reflect the rates observed in clinical practice.

Chronic Hepatitis C

Adult Subjects

In all hepatitis C studies, one or more serious adverse reactions occurred in 10% of CHC monoinfected subjects and in 19% of CHC/HIV subjects receiving PEGASYS alone or in combination with ribavirin. The most common serious adverse reactions (3% in CHC and 5% in CHC/HIV) was bacterial infection (e.g., sepsis, osteomyelitis, endocarditis, pyelonephritis, pneumonia). Other SAEs occurred at a frequency of less than 1% and included: suicide, suicidal ideation, aggression, anxiety, drug abuse and drug overdose, angina, hepatic dysfunction, fatty liver, cholangitis, arrhythmia, diabetes mellitus, autoimmune phenomena (e.g., hyperthyroidism, hypothyroidism, sarcoidosis, systemic lupus erythematosus, rheumatoid arthritis), peripheral neuropathy, aplastic anemia, peptic ulcer, gastrointestinal bleeding, pancreatitis, colitis, corneal ulcer, pulmonary embolism, coma, myositis, cerebral hemorrhage, thrombotic thrombocytopenic purpura, psychotic disorder, and hallucination.

In clinical trials, 98 to 99 percent of subjects experienced one or more adverse reactions. For hepatitis C subjects, the most commonly reported adverse reactions were psychiatric reactions, including depression, insomnia, irritability, anxiety, and flu-like symptoms such as fatigue, pyrexia, myalgia, headache, and rigors. Other common reactions were anorexia, nausea and vomiting, diarrhea, arthralgias, injection site reactions, alopecia, and pruritus. Table 7displays pooled rates of adverse reactions occurring in greater than 5% of subjects in the PEGASYS monotherapy and PEGASYS/ribavirin combination therapy clinical trials.

Overall, 11% of CHC monoinfected subjects receiving 48 weeks of therapy with PEGASYS either alone or in combination with ribavirin discontinued therapy; 16% of CHC/HIV coinfected subjects discontinued therapy. The most common reasons for discontinuation of therapy were psychiatric, flu-like syndrome (e.g., lethargy, fatigue, headache), dermatologic and gastrointestinal disorders, and laboratory abnormalities (thrombocytopenia, neutropenia, and anemia).

Overall, 39% of subjects with CHC or CHC/HIV required modification of PEGASYS and/or ribavirin therapy. The most common reasons for dose modification of PEGASYS in CHC and CHC/HIV subjects was for neutropenia (20% and 27%, respectively) and thrombocytopenia (4% and 6%, respectively). The most common reason for dose modification of ribavirin in CHC and CHC/HIV subjects was anemia (22% and 16%, respectively). PEGASYS dose was reduced in 12% of subjects receiving 1000 mg to 1200 mg ribavirin for 48 weeks and in 7% of subjects receiving 800 mg ribavirin for 24 weeks. Ribavirin dose was reduced in 21% of subjects receiving 1000 mg to 1200 mg ribavirin for 48 weeks and in 12% of subjects receiving 800 mg ribavirin for 24 weeks.

Chronic hepatitis C monoinfected subjects treated for 24 weeks with PEGASYS and 800 mg ribavirin were observed to have lower incidence of serious adverse reactions (3% vs. 10%), Hgb less than 10 g/dL (3% vs. 15%), dose modification of PEGASYS (30% vs. 36%) and ribavirin (19% vs. 38%) and of withdrawal from treatment (5% vs. 15%) compared to subjects treated for 48 weeks with PEGASYS and 1000 mg or 1200 mg ribavirin. The overall incidence of adverse reactions appeared to be similar in the two treatment groups.

Table 7 Adverse Reactions Occurring in Greater Than or Equal to 5% of Subjects in Chronic Hepatitis C Clinical Trials (Pooled Studies 1, 2, 3, and Study 4)
 | CHC Monotherapy (Pooled Studies 1-3) |  | CHC Combination Therapy (Study 4)
Body System | PEGASYS 180 mcg 48 week [Pooled studies 1, 2, and 3] | ROFERON-A Either 3 MIU [An induction dose of 6 million international units (MIU) three times a week for the first 12 weeks followed by 3 million international units three times a week for 36 weeks given subcutaneously.] or 6/3 MIUof ROFERON-A 48 week | PEGASYS 180 mcg + 1000 mg or 1200 mg Ribavirin 48 week [Study 4] | Intron®A + 1000 mg or 1200 mg Rebetol® 48 week
 | N=559 | N=554 | N=451 | N=443
 | % | % | % | %
Application Site Disorders
Injection site reaction | 22 | 18 | 23 | 16
Endocrine Disorders
Hypothyroidism | 3 | 2 | 4 | 5
Flu-like Symptoms and Signs
Fatigue/Asthenia | 56 | 57 | 65 | 68
Pyrexia | 37 | 41 | 41 | 55
Rigors | 35 | 44 | 25 | 37
Pain | 11 | 12 | 10 | 9
Gastrointestinal
Nausea/Vomiting | 24 | 33 | 25 | 29
Diarrhea | 16 | 16 | 11 | 10
Abdominal pain | 15 | 15 | 8 | 9
Dry mouth | 6 | 3 | 4 | 7
Dyspepsia | <1 | 1 | 6 | 5
Hematologic [Severe hematologic abnormalities (lymphocyte less than 500 cells/mm 3; hemoglobin less than 10 g/dL; neutrophil less than 750 cells/mm 3; platelet less than 50,000 cells/mm 3).]
Lymphopenia | 3 | 5 | 14 | 12
Anemia | 2 | 1 | 11 | 11
Neutropenia | 21 | 8 | 27 | 8
Thrombocytopenia | 5 | 2 | 5 | <1
Metabolic and Nutritional
Anorexia | 17 | 17 | 24 | 26
Weight decrease | 4 | 3 | 10 | 10
Musculoskeletal, Connective Tissue and Bone
Myalgia | 37 | 38 | 40 | 49
Arthralgia | 28 | 29 | 22 | 23
Back pain | 9 | 10 | 5 | 5
Neurological
Headache | 54 | 58 | 43 | 49
Dizziness (excluding vertigo) | 16 | 12 | 14 | 14
Memory impairment | 5 | 4 | 6 | 5
Resistance Mechanism Disorders
Overall | 10 | 6 | 12 | 10
Psychiatric
Irritability/Anxiety/Nervousness | 19 | 22 | 33 | 38
Insomnia | 19 | 23 | 30 | 37
Depression | 18 | 19 | 20 | 28
Concentration impairment | 8 | 10 | 10 | 13
Mood alteration | 3 | 2 | 5 | 6
Respiratory, Thoracic and Mediastinal
Dyspnea | 4 | 2 | 13 | 14
Cough | 4 | 3 | 10 | 7
Dyspnea exertional | <1 | <1 | 4 | 7
Skin and Subcutaneous Tissue
Alopecia | 23 | 30 | 28 | 33
Pruritus | 12 | 8 | 19 | 18
Dermatitis | 8 | 3 | 16 | 13
Dry skin | 4 | 3 | 10 | 13
Rash | 5 | 4 | 8 | 5
Sweating increased | 6 | 7 | 6 | 5
Eczema | 1 | 1 | 5 | 4
Visual Disorders
Vision blurred | 4 | 2 | 5 | 2

Pediatric Subjects

In a clinical trial with 114 pediatric subjects (5 to 17 years of age) treated with PEGASYS alone or in combination with ribavirin, dose modifications were required in approximately one-third of subjects, most commonly for neutropenia and anemia. In general, the safety profile observed in pediatric subjects was similar to that seen in adults. In the pediatric study, the most prevalent adverse events in subjects treated with combination therapy for up to 48 weeks with PEGASYS and ribavirin were influenza-like illness (91%), upper respiratory tract infection (60%), headache (64%), gastrointestinal disorder (56%), skin disorder (47%), and injection-site reaction (45%). Seven subjects receiving combination PEGASYS and ribavirin treatment for 48 weeks discontinued therapy for safety reasons (depression, psychiatric evaluation abnormal, transient blindness, retinal exudates, hyperglycemia, type 1 diabetes mellitus, and anemia). Most of the adverse events reported in the study were mild or moderate in severity. Severe adverse events were reported in 2 subjects in the PEGASYS plus ribavirin combination therapy group (hyperglycemia and cholecystectomy).

Table 8 Percentage of Pediatric Subjects with Adverse Reactions [Displayed adverse drug reactions include all grades of reported adverse clinical events considered possibly, probably, or definitely related to study drug.] During First 24 Weeks of Treatment by Treatment Group (in at Least 10% of Subjects)
 | Study NV17424
System Organ Class | PEGASYS 180 mcg/1.73 m^2× BSA + Ribavirin 15 mg/kg (N=55) | PEGASYS 180 mcg/1.73 m^2× BSA + Placebo [Subjects in the PEGASYS plus placebo arm who did not achieve undetectable viral load at week 24 switched to combination treatment thereafter. Therefore, only the first 24 weeks are presented for the comparison of combination therapy with monotherapy.] (N=59)
 | % | %
General disorders and administration site conditions
Influenza like illness | 91 | 81
Injection site reaction | 44 | 42
Fatigue | 25 | 20
Irritability | 24 | 14
Gastrointestinal disorders
Gastrointestinal disorder | 49 | 44
Nervous system disorders
Headache | 51 | 39
Skin and subcutaneous tissue disorders
Rash | 15 | 10
Pruritus | 11 | 12
Musculoskeletal, connective tissue and bone disorders
Musculoskeletal pain | 35 | 29
Psychiatric disorders
Insomnia | 9 | 12
Metabolism and nutrition disorders
Decreased appetite | 11 | 14

In pediatric subjects randomized to combination therapy, the incidence of most adverse reactions were similar for the entire treatment period (up to 48 weeks plus 24 weeks follow-up) in comparison to the first 24 weeks, and increased only slightly for headache, gastrointestinal disorder, irritability and rash. The majority of adverse reactions occurred in the first 24 weeks of treatment.

Growth inhibition in CHC pediatric subjects [see Warnings and Precautions (5.15)] .

Pediatric subjects treated with PEGASYS plus ribavirin combination therapy showed a delay in weight and height increases up to 48 weeks of therapy compared with baseline. Both weight and height for age z-scores as well as the percentiles of the normative population for subject weight and height decreased during treatment. At the end of 2 years follow-up after treatment, most subjects had returned to baseline normative curve percentiles for weight (64thmean percentile at baseline, 60thmean percentile at 2 years post-treatment) and height (54thmean percentile at baseline, 56thmean percentile at 2 years post-treatment). At the end of treatment, 43% (23 of 53) of subjects experienced a weight percentile decrease of more than 15 percentiles, and 25% (13 of 53) experienced a height percentile decrease of more than 15 percentiles on the normative growth curves. At 2 years post-treatment, 16% (6 of 38) of subjects were more than 15 percentiles below their baseline weight curve and 11% (4 of 38) were more than 15 percentiles below their baseline height curve.

Thirty-eight of the 114 subjects enrolled in the long-term follow-up study extending up to 6 years post-treatment. For most subjects, post-treatment recovery in growth at 2 years post-treatment was maintained to 6 years post-treatment.

CHC with HIV Coinfection (Adults)

The adverse reaction profile of coinfected subjects treated with PEGASYS/ribavirin in Study 7 was generally similar to that shown for monoinfected subjects in Study 4 (Table 7). Events occurring more frequently in coinfected subjects were neutropenia (40%), anemia (14%), thrombocytopenia (8%), weight decrease (16%), and mood alteration (9%).

Chronic Hepatitis B

Adult Subjects

In clinical trials of 48 week treatment duration, the adverse reaction profile of PEGASYS in CHB was similar to that seen in CHC PEGASYS monotherapy use, except for exacerbations of hepatitis [see Warnings and Precautions (5.9)] . Six percent of PEGASYS-treated subjects in the hepatitis B studies experienced one or more serious adverse reactions.

The most common or important serious adverse reactions, all of which occurred at a frequency of less than or equal to 1%, in the hepatitis B studies were infections (sepsis, appendicitis, tuberculosis, influenza), hepatitis B flares, and thrombotic thrombocytopenic purpura.

One serious adverse reaction of anaphylactic shock occurred in a dose ranging study of 191 subjects in a subject taking a higher than the approved dose of PEGASYS.

The most commonly observed adverse reactions in the PEGASYS and lamivudine groups, respectively, were pyrexia (54% vs. 4%), headache (27% vs. 9%), fatigue (24% vs. 10%), myalgia (26% vs. 4%), alopecia (18% vs. 2%), and anorexia (16% vs. 3%).

Overall 5% of hepatitis B subjects discontinued PEGASYS therapy and 40% of subjects required modification of PEGASYS dose. The most common reason for dose modification in subjects receiving PEGASYS therapy was for laboratory abnormalities including neutropenia (20%), thrombocytopenia (13%), and ALT elevation (11%).

Pediatric Subjects

In a clinical trial with 111 subjects 3 to 17 years of age treated with PEGASYS for 48 weeks, the safety profile was consistent with that seen in adults with CHB and in pediatric subjects with CHC. The most commonly observed adverse reactions in PEGASYS-treated patients were pyrexia (51%), headache (21%), abdominal pain (17%), cough (15%), vomiting (15%), influenza-like illness (14%), alanine aminotransferase increased (10%), aspartate aminotransferase increased (10%), rash (10%), asthenia (9.0%), epistaxis (9.0%), nausea (9.0%), fatigue (8%), upper respiratory tract infection (8%), alopecia (6%), decreased appetite (6%), dizziness (6%), and nasopharyngitis (6%).

Growth inhibition in CHB pediatric subjects [see Warnings and Precautions (5.15)] .

The mean changes from baseline in z-scores for height and weight for age were -0.07 and -0.21 for PEGASYS-treated subjects at Week 48. Comparable findings were observed in untreated patients at Week 48 (changes in z-scores for height and weight for age were -0.01 and -0.08, respectively). At Week 48 of PEGASYS treatment, a height or weight decrease of more than 15 percentiles on the normative growth curves was observed in 6% of subjects for height and 13% of subjects for weight. At 24 weeks after the end of PEGASYS treatment the percentage of subjects with decrease of more than 15 percentiles from baseline was 12% for height and 11% for weight. At 5 years post-treatment, the percentage of subjects with decrease of more than 15 percentiles from baseline was 18% for height and 29% for weight.

Laboratory Values

Adult Subjects

The laboratory test values observed in the hepatitis B trials (except where noted below) were similar to those seen in the PEGASYS monotherapy CHC trials.

Neutrophils

In the hepatitis C studies, decreases in neutrophil count below normal were observed in 95% of all subjects treated with PEGASYS either alone or in combination with ribavirin. Severe potentially life-threatening neutropenia (ANC less than 500 cells/mm^3) occurred in 5% of CHC subjects and 12% of CHC/HIV subjects receiving PEGASYS either alone or in combination with ribavirin. Modification of PEGASYS dose for neutropenia occurred in 17% of subjects receiving PEGASYS monotherapy and 22% of subjects receiving PEGASYS/ribavirin combination therapy. In the CHC/HIV subjects 27% required modification of interferon dosage for neutropenia. Two percent of subjects with CHC and 10% of subjects with CHC/HIV required permanent reductions of PEGASYS dosage and less than 1% required permanent discontinuation. Median neutrophil counts return to pre-treatment levels 4 weeks after cessation of therapy [see Dosage and Administration (2.6)].

Lymphocytes

Decreases in lymphocyte count are induced by interferon alpha therapy. PEGASYS plus ribavirin combination therapy induced decreases in median total lymphocyte counts (56% in CHC and 40% in CHC/HIV, with median decrease of 1170 cells/mm^3in CHC and 800 cells/mm^3in CHC/HIV). In the hepatitis C studies, lymphopenia was observed during both monotherapy (81%) and combination therapy with PEGASYS and ribavirin (91%). Severe lymphopenia (less than 500 cells/mm^3) occurred in approximately 5% of all monotherapy subjects and 14% of all combination PEGASYS and ribavirin therapy recipients. Dose adjustments were not required by protocol. The clinical significance of the lymphopenia is not known.

In CHC with HIV coinfection, CD4 counts decreased by 29% from baseline (median decrease of 137 cells/mm^3) and CD8 counts decreased by 44% from baseline (median decrease of 389 cells/mm^3) in the PEGASYS plus ribavirin combination therapy arm. Median lymphocyte CD4 and CD8 counts return to pre-treatment levels after 4 to 12 weeks of the cessation of therapy. CD4% did not decrease during treatment.

Platelets

In the hepatitis C studies, platelet counts decreased in 52% of CHC subjects and 51% of CHC/HIV subjects treated with PEGASYS alone (respectively median decrease of 41% and 35% from baseline), and in 33% of CHC subjects and 47% of CHC/HIV subjects receiving combination therapy with ribavirin (median decrease of 30% from baseline). Moderate to severe thrombocytopenia (less than 50,000 cells/mm^3) was observed in 4% of CHC and 8% of CHC/HIV subjects. Median platelet counts return to pre-treatment levels 4 weeks after the cessation of therapy.

Hemoglobin

In the hepatitis C studies, the hemoglobin concentration decreased below 12 g/dL in 17% (median Hgb reduction of 2.2 g/dL) of monotherapy and 52% (median Hgb reduction of 3.7 g/dL) of combination therapy subjects. Severe anemia (Hgb less than 10 g/dL) was encountered in 13% of all subjects receiving combination therapy and in 2% of CHC subjects and 8% of CHC/HIV subjects receiving PEGASYS monotherapy. Dose modification for anemia in ribavirin recipients treated for 48 weeks occurred in 22% of CHC subjects and 16% of CHC/HIV subjects [see Dosage and Administration (2.6)].

Triglycerides

Triglyceride levels are elevated in subjects receiving alfa interferon therapy and were elevated in the majority of subjects participating in clinical studies receiving either PEGASYS alone or in combination with ribavirin. Random levels greater than or equal to 400 mg/dL were observed in about 20% of CHC subjects. Severe elevations of triglycerides (greater than 1000 mg/dL) occurred in 2% of CHC monoinfected subjects.

In HCV/HIV coinfected subjects, fasting levels greater than or equal to 400 mg/dL were observed in up to 36% of subjects receiving either PEGASYS alone or in combination with ribavirin. Severe elevations of triglycerides (greater than 1000 mg/dL) occurred in 7% of coinfected subjects.

ALT Elevations

Chronic Hepatitis C

One percent of subjects in the hepatitis C trials experienced marked elevations (5- to 10-fold above the upper limit of normal) in ALT levels during treatment and follow-up. These transaminase elevations were on occasion associated with hyperbilirubinemia and were managed by dose reduction or discontinuation of study treatment. Liver function test abnormalities were generally transient. One case was attributed to autoimmune hepatitis, which persisted beyond study medication discontinuation [see Dosage and Administration (2.6)].

Chronic Hepatitis B

Transient ALT elevations are common during hepatitis B therapy with PEGASYS. Twenty-five percent and 27% of subjects experienced elevations of 5 to 10 × ULN and 12% and 18% had elevations of greater than 10 × ULN during treatment of HBeAg negative and HBeAg positive disease, respectively. Flares have been accompanied by elevations of total bilirubin and alkaline phosphatase and less commonly with prolongation of PT and reduced albumin levels. Eleven percent of subjects had dose modifications due to ALT flares and less than 1% of subjects were withdrawn from treatment [see Warnings and Precautions (5.9)and Dosage and Administration (2.6)].

ALT flares of 5 to 10 × ULN occurred in 13% and 16% of subjects, while ALT flares of greater than 10 × ULN occurred in 7% and 12% of subjects in HBeAg-negative and HBeAg-positive disease, respectively, after discontinuation of PEGASYS therapy.

Thyroid Function

PEGASYS alone or in combination with ribavirin was associated with the development of abnormalities in thyroid laboratory values, some with associated clinical manifestations. In the hepatitis C studies, hypothyroidism or hyperthyroidism requiring treatment, dose modification or discontinuation occurred in 4% and 1% of PEGASYS treated subjects and 4% and 2% of PEGASYS and ribavirin treated subjects, respectively. Approximately half of the subjects, who developed thyroid abnormalities during PEGASYS treatment, still had abnormalities during the follow-up period [see Warnings and Precautions (5.6)] .

Pediatric Subjects

Decreases in hemoglobin, neutrophils and platelets may require dose reduction or permanent discontinuation from treatment in pediatric subjects [see Dosage and Administration (2.3, 2.5, 2.6)] . Most laboratory abnormalities noted during the CHC clinical trial (Table 9) returned to baseline levels shortly after completion of treatment.

Table 9 Selected Hematologic Abnormalities During First 24 Weeks of Treatment by Treatment Group in Previously Untreated Pediatric Subjects with CHC
Laboratory Parameter | PEGASYS 180 mcg/1.73 m^2× BSA + Ribavirin 15 mg/kg (N=55) | PEGASYS 180 mcg/1.73 m^2× BSA + Placebo [Subjects in the PEGASYS plus placebo arm who did not achieve undetectable viral load at week 24 switched to combination treatment thereafter. Therefore, only the first 24 weeks are presented for the comparison of combination therapy with monotherapy.] (N=59)
Neutrophils (cells/mm^3)
1,000 - <1,500 | 31% | 39%
750 - <1,000 | 27% | 17%
500 - <750 | 25% | 15%
<500 | 7% | 5%
Platelets (cells/mm^3)
75,000 - <100,000 | 4% | 2%
50,000 - <75,000 | 0% | 2%
< 50,000 | 0% | 0%
Hemoglobin (g/dL)
8.5-<10 | 7% | 3%
<8.5 | 0% | 0%

In patients randomized to combination therapy, the incidence of abnormalities during the entire treatment phase (up to 48 weeks plus 24 weeks follow-up) in comparison to the first 24 weeks increased slightly for neutrophils between 500 and 1,000 cells/mm^3and hemoglobin values between 8.5 and 10 g/dL. The majority of hematologic abnormalities occurred in the first 24 weeks of treatment.

The hematologic laboratory abnormalities observed in the CHB pediatric trial were similar to those observed in the CHC pediatric trial.

6.2 Immunogenicity

As with all therapeutic proteins, there is potential for immunogenicity. The detection of antibody formation is highly dependent on the sensitivity and specificity of the assay. Additionally, the observed incidence of antibody (including neutralizing antibody) positivity in an assay may be influenced by several factors including assay methodology, sample handling, timing of sample collection, concomitant medications, and underlying disease. For these reasons, comparison of the incidence of antibodies to peginterferon alfa-2a in the studies described below with the incidence of antibodies in other studies or to other products may be misleading.

Chronic Hepatitis C

Nine percent (71/834) of subjects treated with PEGASYS with or without ribavirin developed binding antibodies to interferon alfa-2a, as assessed by an ELISA assay. Three percent of subjects (25/835) receiving PEGASYS with or without ribavirin, developed low-titer neutralizing antibodies (using an assay with a sensitivity of 100 INU/mL).

Chronic Hepatitis B

Twenty-nine percent (42/143) of hepatitis B subjects treated with PEGASYS for 24 weeks developed binding antibodies to interferon alfa-2a, as assessed by an ELISA assay. Thirteen percent of subjects (19/143) receiving PEGASYS developed low-titer neutralizing antibodies (using an assay with a sensitivity of 100 INU/mL).

The clinical and pathological significance of the appearance of serum neutralizing antibodies is unknown. No apparent correlation of antibody development to clinical response or adverse events was observed. The percentage of subjects whose test results were considered positive for antibodies is highly dependent on the sensitivity and specificity of the assays.

6.3 Postmarketing Experience

The following adverse reactions have been identified and reported during post-approval use of PEGASYS therapy. Because these reactions are reported voluntarily from a population of uncertain size, it is not always possible to reliably estimate their frequency or establish a causal relationship to drug exposure.

Blood and lymphatic system disorders:pure red cell aplasia

Ear and labyrinth disorders:hearing impairment, hearing loss

Gastrointestinal disorders:tongue pigmentation

Immune system disorders:liver graft rejection and renal graft rejection [see Use in Specific Populations (8.8)]

Infections and infestations:limb abscess

Metabolism and nutrition disorders:dehydration

Skin and subcutaneous tissue disorders:serious skin reactions

Neurological:seizures

7 DRUG INTERACTIONS

7.1 Drugs Metabolized by Cytochrome P450

There was no effect on the pharmacokinetics of representative drugs metabolized by CYP 2C9, CYP 2C19, CYP 2D6 or CYP 3A4.

Treatment with PEGASYS once weekly for 4 weeks in healthy subjects was associated with an inhibition of P450 1A2 and a 25% increase in theophylline AUC.

7.2 Theophylline

Treatment with PEGASYS once weekly for 4 weeks in healthy subjects was associated with an inhibition of P450 1A2 and a 25% increase in theophylline AUC. Theophylline serum levels should be monitored and appropriate dose adjustments considered for patients given both theophylline and PEGASYS.

7.3 Methadone

In a PK study of HCV subjects concomitantly receiving methadone, treatment with PEGASYS once weekly for 4 weeks was associated with methadone levels that were 10% to 15% higher than at baseline. The clinical significance of this finding is unknown; however, patients should be monitored for the signs and symptoms of methadone toxicity.

The pharmacokinetics of concomitant administration of methadone and PEGASYS were evaluated in 24 PEGASYS naïve CHC subjects (15 male, 9 female) who received 180 mcg PEGASYS subcutaneously weekly. All subjects were on stable methadone maintenance therapy (median dose 95 mg, range 30 mg to 150 mg) prior to receiving PEGASYS. Mean methadone PK parameters were 10% to 15% higher after 4 weeks of PEGASYS treatment as compared to baseline. Methadone did not significantly alter the PK of PEGASYS as compared to a PK study of 6 chronic hepatitis C subjects not receiving methadone.

7.4 Nucleoside Analogues

NRTIs

In Study 7 among the CHC/HIV coinfected cirrhotic subjects receiving NRTIs cases of hepatic decompensation (some fatal) were observed [see Warnings and Precautions (5.9)] .

Patients receiving PEGASYS/ribavirin in combination with other HCV antiviral drugs and NRTIs should be closely monitored for treatment associated toxicities. Physicians should refer to prescribing information for other HCV antiviral drugs and the respective NRTIs for guidance regarding toxicity management. In addition, dose reduction or discontinuation of PEGASYS, ribavirin or both, should also be considered if worsening toxicities are observed [see Warnings and Precautions (5.3, 5.9)and Dosage and Administration (2.6)] .

Zidovudine

In Study 7, subjects who were administered zidovudine in combination with PEGASYS/ribavirin developed severe neutropenia (ANC less than 500 cells/mm^3) and severe anemia (hemoglobin less than 8 g/dL) more frequently than similar subjects not receiving zidovudine (neutropenia 15% vs. 9%) (anemia 5% vs. 1%). Discontinuation of zidovudine should be considered as medically appropriate. Dose reduction or discontinuation of PEGASYS, ribavirin or both should also be considered if worsening clinical toxicities are observed, including hepatic decompensation (e.g., Child-Pugh greater than 6).

Refer to the prescribing information for specific HCV antiviral drugs used in combination with PEGASYS for information on drug interaction potential.

8 USE IN SPECIFIC POPULATIONS

8.1 Pregnancy

Pregnancy Exposure Registry– Use with ribavirin

A ribavirin Pregnancy Registry has been established to monitor maternal and fetal outcomes of pregnancies of female patients and female partners of male patients exposed to ribavirin during pregnancy or who become pregnant within 6 months following cessation of treatment with ribavirin. Healthcare providers and patients are encouraged to report such cases by calling 1-800-593-2214.

Risk Summary

There are no adequate and well-controlled studies of PEGASYS in pregnant women to inform a drug-associated risk. Based on animal reproduction studies, PEGASYS can cause fetal harm and should be assumed to have abortifacient potential. Non-pegylated interferon alfa-2a treatment caused abortion when given to pregnant rhesus monkeys (see Data). The background risk of major birth defects and miscarriage in the indicated population is 3% and 4-22%, respectively. In the U.S. general population, the estimated background risk for major birth defects and miscarriage in the clinically recognized pregnancies is 2-4% and 15-20%, respectively.

PEGASYS combination treatment with ribavirin is contraindicated in women who are pregnant and in the male partners of women who are pregnant [see Contraindications (4), Warnings and Precautions (5.1), and ribavirin labeling] . Significant teratogenic and/or embryocidal effects have been demonstrated in all animal species exposed to ribavirin [see ribavirin labeling].

Data

Animal Data –Groups of 8 or 9 pregnant rhesus monkeys were given non-pegylated interferon alfa-2a by daily intramuscular injection over days 22 to 70 of gestation at doses of 1, 5 and 25 million IU/day. Two, 3 and 6 monkeys aborted in the low, mid and high dose groups compared with 1 in the control group. Maternal toxicity, characterized by transient body weight loss, was seen at all dose levels. There were too few remaining pregnancies to assess teratogenic potential but no developmental abnormalities were observed in surviving fetuses.

8.2 Lactation

There is no information regarding the presence of peginterferon alfa-2a in human milk, the effects on the breastfed infant, or the effects on milk production. Because of the potential for adverse reactions from the drugs in nursing infants, a decision must be made whether to discontinue nursing or discontinue PEGASYS. The developmental and health benefits of breastfeeding should be considered along with the mother's clinical need for PEGASYS and any potential adverse effects on the breastfed child from PEGASYS or from the underlying maternal condition.

The Centers for Disease Control and Prevention recommends that HIV-infected mothers not breastfeed their infants to avoid potential transmission of HIV; therefore, CHC- and CHB-infected mothers coinfected with HIV should not breastfeed their infants.

8.3 Females and Males of Reproductive Potential

Pregnancy Testing

Females of reproductive potential must undergo pregnancy testing before initiation of treatment with PEGASYS or with PEGASYS in combination with ribavirin or with other HCV drugs [see Warnings and Precautions (5.17)] .

Females of reproductive potential receiving PEGASYS in combination with ribavirin must have a routine pregnancy test performed monthly during treatment and for at least 6 months following treatment. Female partners of male patients receiving PEGASYS in combination with ribavirin must have a routine pregnancy test performed monthly during treatment and for at least 6 months posttherapy [see Warnings and Precautions (5.17), ribavirin prescribing information] .

Contraception

Females

Because of the abortifacient potential of PEGASYS, females of reproductive potential should be advised to use effective contraception during therapy [see Warnings and Precautions (5.17)] . However, when receiving PEGASYS in combination with ribavirin, women of reproductive potential and their partners must use effective contraception during treatment and for at least 6 months after the last dose [see ribavirin prescribing information].

Infertility

Females

Based on its mechanism of action and studies in female monkeys, PEGASYS can cause disruption of the menstrual cycle [see Nonclinical Toxicology (13.1)] . No female fertility study has been performed.

8.4 Pediatric Use

PEGASYS is indicated for the treatment of CHC in pediatric patients 5 to 17 years of age and for the treatment of CHB in pediatric patients 3 to 17 years of age [see Indications and Usage (1.1), (1.2), Dosage and Administration (2.3), (2.5), Clinical Studies (14.1), (14.4)].

The use of PEGASYS for the treatment of pediatric patients 5 to 17 years of age with CHC is based on one clinical trial in 114 previously untreated CHC subjects 5 to 17 years of age with compensated liver disease and detectable HCV RNA [see Clinical Trials Experience (6.1), Clinical Studies (14.1)] . The safety and efficacy of PEGASYS in pediatric patients with CHC below the age of 5 years have not been established.

The use of PEGASYS for the treatment of pediatric patients 3 to 17 years of age with CHB is based on one clinical trial in 161 previously untreated CHB subjects 3 to 17 years of age of whom 111 were assigned to treatment with PEGASYS [see Clinical Trials Experience (6.1), Clinical Studies (14.4)] . PEGASYS has not been studied in pediatric CHB patients with liver cirrhosis and the safety and efficacy of PEGASYS in pediatric patients with CHB below the age of 3 years have not been established.

PEGASYS contains benzyl alcohol. In neonates and infants, benzyl alcohol has been reported to be associated with an increased incidence of neurological and other complications which are sometimes fatal in neonates and infants [see Contraindications (4)] .

8.5 Geriatric Use

Younger patients have higher virologic response rates than older patients. Clinical studies of PEGASYS alone or in combination with ribavirin did not include sufficient numbers of subjects aged 65 or over to determine whether they respond differently from younger subjects. Adverse reactions related to alpha interferons, such as CNS, cardiac, and systemic (e.g., flu-like) effects may be more severe in the elderly and caution should be exercised in the use of PEGASYS in this population. PEGASYS is excreted by the kidney, and the risk of toxic reactions to this therapy may be greater in patients with impaired renal function. Because elderly patients are more likely to have decreased renal function, care should be taken in dose selection and it may be useful to monitor renal function. PEGASYS should be used with caution in patients with creatinine clearance less than or equal to 50 mL/min. The dose of PEGASYS should be reduced for patients with creatinine clearance less than 30 mL/min [see Dosage and Administration (2.6)and Use in Specific Populations (8.7)] .

8.6 Hepatic Impairment

CHC patients with cirrhosis may be at risk of hepatic decompensation and death when treated with alpha interferons, including PEGASYS. During treatment, patients' clinical status and hepatic function should be closely monitored, and PEGASYS treatment should be immediately discontinued if decompensation (Child-Pugh score greater than or equal to 6) is observed [see Contraindications (4)] . Chronic hepatitis B subjects experienced transient acute exacerbations (flares) of hepatitis B (ALT elevation greater than 10-fold higher than the upper limit of normal) during PEGASYS treatment (12% and 18%) and post-treatment (7% and 12%) in HBeAg-negative and HBeAg-positive subjects, respectively.

8.7 Renal Impairment

Renal function should be evaluated in all patients prior to initiation of PEGASYS by estimating the patient's creatinine clearance.

A clinical trial evaluated treatment with PEGASYS and ribavirin in 50 CHC subjects with moderate (creatinine clearance 30 – 50 mL/min) or severe (creatinine clearance less than 30 mL/min) renal impairment or end stage renal disease (ESRD) requiring chronic hemodialysis (HD). In 18 subjects with ESRD receiving chronic HD, PEGASYS was administered at a dose of 135 mcg once weekly. Dose reductions and temporary interruptions of PEGASYS (due to PEGASYS-related adverse reactions, mainly anemia) were observed in up to 22% ESRD/HD subjects during treatment; and 17% of these subjects discontinued PEGASYS due to PEGASYS-related adverse reactions. Only one-third of ESRD/HD subjects received PEGASYS for 48 weeks. Subjects with severe (n=14) or moderate (n=17) renal impairment received PEGASYS 180 mcg once weekly. PEGASYS discontinuation rates were 36% and 0% in subjects with severe and moderate renal impairment, respectively, compared to 0% discontinuation rate in subjects with normal renal function.

Based on the pharmacokinetic and safety results from this trial, patients with creatinine clearance less than 30 mL/min should receive a reduced dose of PEGASYS. In addition, patients with any degree of renal impairment should be carefully monitored for laboratory abnormalities (especially decreased hemoglobin) and adverse reactions, and should undergo careful monitoring of creatinine clearance. Patients with clinically significant laboratory abnormalities or adverse reactions which are persistently severe or worsening should have therapy withdrawn [see Dosage and Administration (2.6), Clinical Pharmacology (12.3)] . Refer to the prescribing information for specific HCV antiviral drugs used in combination with PEGASYS for information on use in patients with renal impairment.

8.8 Organ Transplant Recipients

The safety and efficacy of PEGASYS treatment have not been established in patients with liver and other transplantations. As with other alpha interferons, liver and renal graft rejections have been reported on PEGASYS.

8.9 Chronic Hepatitis B

The safety and efficacy of PEGASYS have not been established in:

- Hepatitis B patients coinfected with HCV or HIV
- Hepatitis C patients coinfected with HBV or coinfected with HIV with a CD4+ cell count less than 100 cells/mm^3

10 OVERDOSAGE

There is limited experience with overdosage. The maximum dose received by any patient was 7 times the intended dose of PEGASYS (180 mcg/day for 7 days). There were no serious reactions attributed to overdosages. Weekly doses of up to 630 mcg have been administered to patients with cancer. Dose-limiting toxicities were fatigue, elevated liver enzymes, neutropenia, and thrombocytopenia. There is no specific antidote for PEGASYS. Hemodialysis and peritoneal dialysis are not effective.

11 DESCRIPTION

Peginterferon alfa-2a, is a covalent conjugate of recombinant alfa-2a interferon (approximate molecular weight [MW] 20,000 daltons) with a single branched bis-monomethoxy polyethylene glycol (PEG) chain (approximate MW 40,000 daltons). The PEG moiety is linked at a single site to the interferon alfa moiety via a stable amide bond to lysine. Peginterferon alfa-2a has an approximate molecular weight of 60,000 daltons. Interferon alfa-2a is produced using recombinant DNA technology in which a cloned human leukocyte interferon gene is inserted into and expressed in Escherichia coli.

PEGASYS is a sterile, preservative-free, colorless to slightly yellowish solution available as an injection and is administered subcutaneously.

Each vial of 180 mcg/mL peginterferon alfa-2a (expressed as the amount of interferon alfa-2a) also contains acetic acid (0.05 mg), benzyl alcohol (10 mg), polysorbate 80 (0.05 mg), sodium acetate trihydrate (2.62 mg), and sodium chloride (8 mg) at pH 6 ± 0.5.

Each prefilled syringe of 180 mcg/0.5 mL peginterferon alfa-2a (expressed as the amount of interferon alfa-2a) also contains acetic acid (0.0231 mg), benzyl alcohol (5 mg), polysorbate 80 (0.025 mg), sodium acetate trihydrate (1.3085 mg), and sodium chloride (4 mg) at pH 6 ± 0.5.

12 CLINICAL PHARMACOLOGY

12.1 Mechanism of Action

Pegylated recombinant human interferon alfa-2a is an inducer of the innate antiviral immune response [see Microbiology (12.4)] .

12.2 Pharmacodynamics

PEGASYS stimulates the production of effector proteins such as serum neopterin and 2', 5'-oligoadenylate synthetase.

12.3 Pharmacokinetics

Maximal serum concentrations (Cmax) and AUC increased in a nonlinear dose related manner following administration of 90 to 270 mcg of PEGASYS. Maximal serum concentrations (Cmax) occur between 72 to 96 hours post-dose.

Week 48 mean trough concentrations (16 ng/mL; range 4 to 28) at 168 hours post-dose are approximately 2-fold higher than week 1 mean trough concentrations (9 ng/mL; range 0 to 15). Steady-state serum levels are reached within 5 to 8 weeks of once weekly dosing. The peak to trough ratio at week 48 is approximately 2. The mean systemic clearance in healthy subjects given PEGASYS was 94 mL/h, which is approximately 100-fold lower than that for interferon alfa-2a (ROFERON®-A). The mean terminal half-life after subcutaneous dosing in subjects with chronic hepatitis C was 160 hours (range 84 to 353 hours) compared to 5 hours (range 3.7 to 8.5 hours) for ROFERON-A.

Specific Populations

Gender and Age

PEGASYS administration yielded similar pharmacokinetics in male and female healthy subjects. The AUC was increased from 1295 to 1663 ng∙h/mL in subjects older than 62 years taking 180 mcg PEGASYS, but peak concentrations were similar (9 vs. 10 ng/mL) in those older and younger than 62 years.

Pediatric Patients

In a population pharmacokinetics study, 14 children 2 to 8 years of age with CHC received PEGASYS based on their body surface area (BSA of the child × 180 mcg/1.73 m^2). The clearance of PEGASYS in children was nearly 4-fold lower compared to the clearance reported in adults.

Steady-state trough levels in children with the BSA-adjusted dosing were similar to trough levels observed in adults with 180 mcg fixed dosing. Time to reach the steady state in children is approximately 12 weeks, whereas in adults, steady state is reached within 5 to 8 weeks. In these children receiving the BSA adjusted dose, the mean exposure (AUC) during the dosing interval is predicted to be 25% to 70% higher than that observed in adults receiving 180 mcg fixed dosing.

Based on the population pharmacokinetic model including data from 30 pediatric CHB patients who received the BSA based dosing regimen [see Dosage and Administration (2.5)] , AUC values in pediatric CHB patients were comparable with that observed in adults receiving 180 mcg dosing.

Renal Impairment

A clinical trial evaluated 50 CHC subjects with either moderate (creatinine clearance 30 to 50 mL/min) or severe (creatinine clearance less than 30 mL/min) renal impairment or end stage renal disease (ESRD) requiring chronic hemodialysis (HD). Subjects with moderate renal impairment receiving PEGASYS 180 mcg once weekly dose exhibited similar peginterferon alfa-2a plasma exposures compared to subjects with normal renal function (creatinine clearance greater than 80 mL/min) receiving the standard dose of PEGASYS. No PEGASYS dose adjustment is required for patients with mild or moderate renal impairment [see Dosage and Administration (2.6)and Use in Specific Populations (8.7)] .

For subjects with severe renal impairment, peginterferon alfa-2a apparent clearance was 43% lower as compared to subjects with normal renal function. A reduced dose of 135 mcg once weekly PEGASYS is recommended in patients with severe renal impairment. This dose may result in 30% higher peginterferon alfa-2a exposure compared to that of the recommended dose for patients with normal renal function. Signs and symptoms of interferon toxicity should be closely monitored in patients with severe renal impairment and the dose reduced to 90 mcg once weekly as appropriate [see Dosage and Administration (2.6)and Use in Specific Populations (8.7)] .

In 18 subjects with ESRD receiving chronic HD, PEGASYS was administered at a dose of 135 mcg once weekly. The apparent clearance of peginterferon alfa-2a was similar between subjects with ESRD and subjects with normal renal function. Despite a lower exposure to peginterferon alfa-2a with the 135 mcg dose, subjects with ESRD had a high rate of adverse events and discontinuations of PEGASYS in the trial. Therefore, a dose of 135 mcg once weekly should be used for patients with ESRD on HD. However, the potential for reduced efficacy and increased interferon toxicity in patients with ESRD receiving chronic HD should be closely monitored. The dose may be reduced to 90 mcg once weekly as appropriate [see Dosage and Administration (2.6)and Use in Specific Populations (8.7)] .

12.4 Microbiology

Mechanism of Action

The biological activity of PEGASYS is derived from its recombinant human interferon α-2a moiety. Peginterferon α-2a binds to the human type 1 interferon receptor leading to receptor dimerization. Receptor dimerization activates multiple intracellular signal transduction pathways initially mediated by the JAK/STAT pathway. Given the diversity of cell types that respond to interferon α-2a, and the multiplicity of potential intracellular responses to interferon receptor activation, peginterferon α-2a is expected to have pleiotropic biological effects in the body.

Activity against HCV

Antiviral Activity in Cell Culture

In the stable HCV cell culture model system (HCV replicon), peginterferon α-2a inhibited HCV RNA replication, with an EC50value of 0.1-3 ng/mL (0.083 – 2.49 IU/mL). The combination of peginterferon α-2a and ribavirin was more effective at inhibiting HCV RNA replication than either agent alone.

Resistance

Different HCV genotypes display considerable clinical variability in their response to peginterferon-α and ribavirin therapy. Viral genetic determinants associated with the variable response have not been definitively identified.

Cross-resistance

Cross-resistance between interferon-α, ribavirin, and direct-acting HCV antiviral drugs is unlikely based on their mechanisms of action.

Host Factors Affecting Response

Polymorphisms in the IL28B gene have been shown to impact the response to peginterferon α-2a. Determining the IL28B genotype should be considered.

Activity against HBV

Antiviral Activity in Cell Culture and Animal Model

The antiviral activity of interferon α-2a (standard and pegylated) has been demonstrated using an HBV cell culture system and a mouse model. In human hepatoma cells (HepG2 and Huh7) transiently transfected with HBV, interferon α-2a (parent compound of PEGASYS) at a 1,000 IU/mL (6.25 ng/mL) concentration was active against all 4 major HBV genotypes (A, B, C and D) with a more pronounced effect on genotypes A and B isolates versus genotypes C and D isolates (after 3 days post-transfection, approximately 2 log10copies/mL versus approximately 1 log10copies/mL reduction in HBV DNA levels). In mice with HBV infection established by hydrodynamic injection of HBV DNA, peginterferon α-2a at a 3 µg/kg dose was active against all 4 major HBV genotypes with a more pronounced effect on genotypes A and B isolates versus genotypes C and D isolates (approximately 2 log10copies/mL versus approximately 1 log10copies/mL reduction in HBV DNA levels after 3 and 7 days post-infection).

Resistance

Differences in the clinical response to interferon-based therapy have been observed depending on HBV genotype. Although efficacy was demonstrated in all HBV genotypes, genotypes A and B were associated with greater efficacy responses than genotypes C and D (the lowest response being observed with genotype D). In addition, HBV gene mutations may affect interferon therapy response such as viral mutations in the precore (PC) and basal core promoter (BCP) regions.

Cross-resistance

Cross-resistance between interferon α and direct-acting HBV antiviral drugs is unlikely based on their mechanisms of action.

13 NONCLINICAL TOXICOLOGY

13.1 Carcinogenesis, Mutagenesis, Impairment of Fertility

Carcinogenesis

PEGASYS has not been tested for its carcinogenic potential.

Use with other HCV antiviral drugs:Refer to the prescribing information for specific antiviral drugs used in combination with PEGASYS for additional warnings

Mutagenesis

PEGASYS did not cause DNA damage when tested in the Ames bacterial mutagenicity assay and in the in vitrochromosomal aberration assay in human lymphocytes, either in the presence or absence of metabolic activation.

Use with other HCV antiviral drugs:Refer to the prescribing information for specific HCV antiviral drugs used in combination with PEGASYS for additional warnings.

Impairment of Fertility

PEGASYS may impair fertility in women. Prolonged menstrual cycles and/or amenorrhea were observed in female cynomolgus monkeys given subcutaneous injections of 600 mcg/kg/dose (7200 mcg/m^2/dose) of PEGASYS every other day for one month, at approximately 180 times the recommended weekly human dose for a 60 kg person (based on body surface area). Menstrual cycle irregularities were accompanied by both a decrease and delay in the peak 17β-estradiol and progesterone levels following administration of PEGASYS to female monkeys. A return to normal menstrual rhythm followed cessation of treatment. Every other day dosing with 100 mcg/kg (1200 mcg/m^2) PEGASYS (equivalent to approximately 30 times the recommended human dose) had no effects on cycle duration or reproductive hormone status.

The effects of PEGASYS on male fertility have not been studied. However, no adverse effects on fertility were observed in male Rhesus monkeys treated with non-pegylated interferon alfa-2a for 5 months at doses up to 25 × 10^6IU/kg/day.

Use with other HCV antiviral drugs:Refer to the prescribing information for specific HCV antiviral drugs used in combination with PEGASYS for additional warnings.

14 CLINICAL STUDIES

14.1 Chronic Hepatitis C Studies 1, 2, and 3: PEGASYS/Ribavirin Combination Therapy

Adult Patients

The safety and effectiveness of PEGASYS in combination with ribavirin for the treatment of hepatitis C virus infection were assessed in two randomized controlled clinical trials. All subjects were adults, had compensated liver disease, detectable hepatitis C virus, liver biopsy diagnosis of chronic hepatitis, and were previously untreated with interferon. Approximately 20% of subjects in both studies had compensated cirrhosis (Child-Pugh class A). Subjects coinfected with HIV were excluded from these studies.

In Study 1, subjects were randomized to receive either PEGASYS 180 mcg subcutaneous once weekly with an oral placebo, PEGASYS 180 mcg once weekly with ribavirin 1000 mg by mouth (body weight less than 75 kg) or 1200 mg by mouth (body weight greater than or equal to 75 kg) or Rebetron®(interferon alfa-2b 3 MIU subcutaneous three times a week plus ribavirin 1000 mg or 1200 mg by mouth). All subjects received 48 weeks of therapy followed by 24 weeks of treatment-free follow-up. Ribavirin or placebo treatment assignment was blinded. Sustained virological response was defined as undetectable (less than 50 IU/mL) HCV RNA on or after study week 68. PEGASYS in combination with ribavirin resulted in a higher SVR compared to PEGASYS alone or interferon alfa-2b and ribavirin (Table 10). In all treatment arms, subjects with viral genotype 1, regardless of viral load, had a lower response rate.

Table 10 Sustained Virologic Response to Combination Therapy (Study 1)
 | Interferon alfa-2b + Ribavirin 1000 mg or 1200 mg | PEGASYS + Placebo | PEGASYS + Ribavirin 1000 mg or 1200 mg
All subjects | 197/444 (44%) [Difference in overall treatment response (PEGASYS/ribavirin – Interferon alfa-2b/ribavirin) was 9% (95% CI 2.3, 15.3).] | 65/224 (29%) | 241/453 (53%)
Genotype 1 | 103/285 (36%) | 29/145 (20%) | 132/298 (44%)
Genotypes 2-6 | 94/159 (59%) | 36/79 (46%) | 109/155 (70%)

In Study 2 (see Table 11), all subjects received PEGASYS 180 mcg subcutaneous once weekly and were randomized to treatment for either 24 or 48 weeks and to a ribavirin dose of either 800 mg or 1000 mg/1200 mg (for body weight less than 75 kg/greater than or equal to 75 kg). Assignment to the four treatment arms was stratified by viral genotype and baseline HCV viral titer. Subjects with genotype 1 and high viral titer (defined as greater than 2 × 10^6HCV RNA copies/mL serum) were preferentially assigned to treatment for 48 weeks.

HCV Genotypes

HCV 1 and 4 – Irrespective of baseline viral titer, treatment for 48 weeks with PEGASYS and 1000 mg or 1200 mg of ribavirin resulted in higher SVR (defined as undetectable HCV RNA at the end of the 24-week treatment-free follow-up period) compared to shorter treatment (24 weeks) and/or 800 mg ribavirin.

HCV 2 and 3 – Irrespective of baseline viral titer, treatment for 24 weeks with PEGASYS and 800 mg of ribavirin resulted in a similar SVR compared to longer treatment (48 weeks) and/or 1000 mg or 1200 mg of ribavirin (see Table 11).

The numbers of subjects with genotype 5 and 6 were too few to allow meaningful assessment.

Table 11 Sustained Virologic Response as a Function of Genotype (Study 2)
 | 24 Weeks Treatment |  | 48 Weeks Treatment
 | PEGASYS + Ribavirin 800 mg (N=207) | PEGASYS + Ribavirin 1000 mg or 1200 mg [1000 mg for body weight less than 75 kg; 1200 mg for body weight greater than or equal to 75 kg.] (N=280) | PEGASYS + Ribavirin 800 mg (N=361) | PEGASYS + Ribavirin 1000 mg or 1200 mg (N=436)
Genotype 1 | 29/101 (29%) | 48/118 (41%) | 99/250 (40%) | 138/271 (51%)
Genotypes 2, 3 | 79/96 (82%) | 116/144 (81%) | 75/99 (76%) | 117/153 (76%)
Genotype 4 | 0/5 (0%) | 7/12 (58%) | 5/8 (63%) | 9/11 (82%)

Other Treatment Response Predictors

Treatment response rates are lower in subjects with poor prognostic factors receiving pegylated interferon alpha therapy. In studies 1 and 2, treatment response rates were lower in subjects older than 40 years (50% vs. 66%), in subjects with cirrhosis (47% vs. 59%), in subjects weighing over 85 kg (49% vs. 60%), and in subjects with genotype 1 with high vs. low viral load (43% vs. 56%). African-American subjects had lower response rates compared to Caucasians.

Paired liver biopsies were performed on approximately 20% of subjects in studies 4 and 5. Modest reductions in inflammation compared to baseline were seen in all treatment groups.

In studies 1 and 2, lack of early virologic response by 12 weeks (defined as HCV RNA undetectable or greater than 2 log10lower than baseline) was grounds for discontinuation of treatment. Of subjects who lacked an early viral response by 12 weeks and completed a recommended course of therapy despite a protocol-defined option to discontinue therapy, 5/39 (13%) achieved an SVR. Of subjects who lacked an early viral response by 24 weeks, 19 completed a full course of therapy and none achieved an SVR.

Pediatric Patients

Previously untreated pediatric subjects 5 through 17 years of age (55% less than 12 years old) with CHC, compensated liver disease and detectable HCV RNA were treated with ribavirin approximately 15 mg/kg/day plus PEGASYS 180 mcg/1.73 m^2× body surface area once weekly for 48 weeks. All subjects were followed for 24 weeks post-treatment. Sustained virological response (SVR) was defined as undetectable (less than 50 IU/mL) HCV RNA on or after study week 68. A total of 114 subjects were randomized to receive either combination treatment of ribavirin plus PEGASYS or PEGASYS monotherapy; subjects failing PEGASYS monotherapy at 24 weeks or later could receive open-label ribavirin plus PEGASYS. The initial randomized arms were balanced for demographic factors; 55 subjects received initial combination treatment of ribavirin plus PEGASYS and 59 received PEGASYS plus placebo; in the overall intent-to-treat population, 45% were female, 80% were Caucasian, and 81% were infected with HCV genotype 1. The SVR results are summarized in Table 12.

Table 12 Sustained Virologic Response in Pediatric Subjects (NV17424 - Study 3)
 | PEGASYS 180 mcg/1.73 m^2× BSA + Ribavirin 15 mg/kg (N=55) [Results indicate undetectable HCV-RNA defined as HCV RNA less than 50 IU/mL at 24 weeks post-treatment using the AMPLICOR HCV test v2.] | PEGASYS 180 mcg/1.73 m^2× BSA + Placebo (N=59)
All HCV genotypes [Scheduled treatment duration was 48 weeks regardless of the genotype] | 29 (53%) | 12 (20%)
HCV genotype 1 | 21/45 (47%) | 8/47 (17%)
HCV non-genotype 1 [Includes HCV genotypes 2, 3 and others] | 8/10 (80%) | 4/12 (33%)

14.2 Chronic Hepatitis C and Coinfection with HIV (CHC/HIV) Study 4: PEGASYS Monotherapy and PEGASYS/Ribavirin Combination Therapy

In Study 4, subjects with CHC/HIV were randomized to receive either PEGASYS 180 mcg subcutaneous once weekly plus an oral placebo, PEGASYS 180 mcg once weekly plus ribavirin 800 mg by mouth daily or ROFERON-A (interferon alfa-2a), 3 MIU subcutaneous three times a week plus ribavirin 800 mg by mouth daily. All subjects received 48 weeks of therapy and sustained virologic response (SVR) was assessed at 24 weeks of treatment-free follow-up. Ribavirin or placebo treatment assignment was blinded in the PEGASYS treatment arms. All subjects were adults, had compensated liver disease, detectable hepatitis C virus, liver biopsy diagnosis of chronic hepatitis C, and were previously untreated with interferon. Subjects also had CD4+ cell count greater than or equal to 200 cells/mm^3or CD4+ cell count greater than or equal to 100 cells/mm^3but less than 200 cells/mm^3and HIV-1 RNA less than 5,000 cells/mm^3, and stable status of HIV. Approximately 15% of subjects in the study had cirrhosis. Results are shown in Table 13.

Table 13 Sustained Virologic Response in Subjects with Chronic Hepatitis C Coinfected with HIV (Study 4)
 | ROFERON-A + Ribavirin 800 mg (N=289) | PEGASYS + Placebo (N=289) | PEGASYS + Ribavirin 800 mg (N=290)
All subjects | 33 (11%) | 58 (20%) | 116 (40%)
Genotype 1 | 12/171 (7%) | 24/175 (14%) | 51/176 (29%)
Genotypes 2, 3 | 18/89 (20%) | 32/90 (36%) | 59/95 (62%)

Treatment response rates are lower in CHC/HIV subjects with poor prognostic factors (including HCV genotype 1, HCV RNA greater than 800,000 IU/mL, and cirrhosis) receiving pegylated interferon alpha therapy. Geographic region is not a prognostic factor for response. However, poor prognostic factors occur more frequently in the US population than in the non-US population.

Of the subjects who did not demonstrate either undetectable HCV RNA or at least a 2 log10reduction from baseline in HCV RNA titer by 12 weeks of PEGASYS and ribavirin combination therapy, 2% (2/85) achieved an SVR.

In CHC subjects with HIV coinfection who received 48 weeks of PEGASYS alone or in combination with ribavirin treatment, mean and median HIV RNA titers did not increase above baseline during treatment or 24 weeks post-treatment.

14.3 Chronic Hepatitis C Studies 5, 6, and 7: PEGASYS Monotherapy

The safety and effectiveness of PEGASYS for the treatment of hepatitis C virus infection were assessed in three randomized, open-label, active-controlled clinical studies. All subjects were adults, had compensated liver disease, detectable hepatitis C virus (HCV), liver biopsy diagnosis of chronic hepatitis, and were previously untreated with interferon. All subjects received therapy by subcutaneous injection for 48 weeks, and were followed for an additional 24 weeks to assess the durability of response. In studies 5 and 6, approximately 20% of subjects had cirrhosis or bridging fibrosis. Study 7 enrolled subjects with a histological diagnosis of cirrhosis (78%) or bridging fibrosis (22%).

In Study 5 (n=630), subjects received either ROFERON-A (interferon alfa-2a) 3 MIU three times a week, PEGASYS 135 mcg once weekly or PEGASYS 180 mcg once weekly. In Study 6 (n=526), subjects received either ROFERON-A 6 MIU three times a week for 12 weeks followed by 3 MIU three times a week for 36 weeks or PEGASYS 180 mcg once weekly. In Study 7 (n=269), subjects received ROFERON-A 3 MIU three times a week, PEGASYS 90 mcg once weekly or PEGASYS 180 mcg once each week.

In all three studies, treatment with PEGASYS 180 mcg resulted in significantly more subjects who experienced a sustained response (defined as undetectable HCV RNA [less than 50 IU/mL] using the COBAS AMPLICOR®HCV Test, version 2 and normalization of ALT on or after study week 68) compared to treatment with ROFERON-A.

In Study 5, response to PEGASYS 135 mcg was not different from response to 180 mcg. In Study 7, response to PEGASYS 90 mcg was intermediate between PEGASYS 180 mcg and ROFERON-A.

Table 14 Sustained Response to Monotherapy Treatment
 | Study 5 |  |  | Study 6 |  |  | Study 7
 | Roferon-A 3 MIU (N=207) | PEGASYS 180 mcg (N=208) | Diff [Percent difference between PEGASYS and ROFERON-A treatment.] (95% CI) | Roferon-A 6/3 MIU [An induction dose of 6 million international units (MIU) three times a week for the first 12 weeks followed by 3 million international units three times a week for 36 weeks given subcutaneously.] (N=261) | PEGASYS 180 mcg (N=265) | Diff (95% CI) | Roferon-A 3 MIU (N=86) | PEGASYS 180 mcg (N=87) | Diff (95% CI)
Combined Virologic and Biologic Sustained Response [Defined as undetectable HCV RNA [less than 50 IU/mL] using the COBAS AMPLICOR ® HCV Test, version 2 and normalization of ALT on or after study week 68.] | 11% | 24% | 13 (6, 20) | 17% | 35% | 18 (11, 25) | 7% | 23% | 16 (6, 26)
Sustained Virologic Response | 11% | 26% | 15 (8, 23) | 19% | 38% | 19 (11, 26) | 8% | 30% | 22 (11, 33)

Matched pre- and post-treatment liver biopsies were obtained in approximately 70% of subjects. Similar modest reductions in inflammation compared to baseline were observed in all treatment groups.

Of the subjects who did not demonstrate either undetectable HCV RNA or at least a 2 log10drop in HCV RNA titer from baseline by 12 weeks of PEGASYS 180 mcg therapy, 2% (3/156) achieved a sustained virologic response [see Dosage and Administration (2.2)] .

Averaged over Study 5, Study 6, and Study 7, response rates to PEGASYS were 23% among subjects with viral genotype 1 and 48% among subjects with other viral genotypes. The treatment response rates were similar in men and women.

14.4 Chronic Hepatitis B Studies 8, 9 and 10: PEGASYS Monotherapy

Adult Patients

The safety and effectiveness of PEGASYS for the treatment of CHB were assessed in controlled clinical trials in HBeAg-positive (Study 8) and HBeAg-negative (Study 9) subjects with CHB.

Subjects were randomized to PEGASYS 180 mcg subcutaneous once weekly, PEGASYS 180 mcg subcutaneous once weekly combined with lamivudine 100 mg once daily by mouth or lamivudine 100 mg once daily by mouth. All subjects received 48 weeks of their assigned therapy followed by 24 weeks of treatment-free follow-up. Assignment to receipt of PEGASYS or no PEGASYS was not masked.

All subjects were adults with compensated liver disease, had chronic hepatitis B virus (HBV) infection, and evidence of HBV replication (serum HBV greater than 500,000 copies/mL for Study 8 and greater than 100,000 copies/mL for Study 9) as measured by PCR (COBAS AMPLICOR®HBV Assay). All subjects had serum alanine aminotransferase (ALT) between 1 and 10 times the upper limit of normal (ULN) and liver biopsy findings compatible with the diagnosis of chronic hepatitis.

The results observed in the PEGASYS and lamivudine monotherapy groups are shown in Table 15.

Table 15 Percentage of Subjects with Serological, Virological, Biochemical, and Histological Response
 | Study 8 HBeAg positive |  |  | Study 9 HBeAg negative
 | Lamivudine N = 272 |  | PEGASYS N = 271 | Lamivudine N = 181 |  | PEGASYS N = 177
 | EOT [End of Treatment (week 48)] | EOF [End of follow-up – 24 weeks post-treatment (week 72)] | EOF | EOT | EOF | EOF
HBeAg Seroconversion (%) | 20 | 19 | 32 | NA | NA | NA
HBV DNA Response (%) [Less than 100,000 copies/mL for HBeAg positive and less than 20,000 copies/mL for HBeAg negative subjects] | 62 | 22 | 32 | 85 | 29 | 43
ALT Normalization (%) | 62 | 28 | 41 | 73 | 44 | 59
HBsAg Seroconversion (%) | 0 | 0 | 3 | 1 | 0 | 3
 | N = 184 |  | N = 207 | N = 125 |  | N = 143
Histological Improvement (%) [Greater than or equal to 2 point decrease in Ishak necro-inflammatory score from baseline with no worsening of the Ishak fibrosis score. Not all subjects provided both initial and end of follow-up biopsies (missing biopsy rates: 19% to 24% in the PEGASYS and 31% to 32% in the lamivudine arms)] | ND | 40 | 41 | ND | 41 | 48
Changes in Ishak fibrosis score compared to baseline (%):
- Improved [Change of 1 point or more in Ishak fibrosis score] | ND | 32 | 25 | ND | 31 | 32
- Unchanged |  | 20 | 25 |  | 23 | 30
- Worsened |  | 16 | 26 |  | 15 | 19

PEGASYS co-administered with lamivudine did not result in any additional sustained response when compared to PEGASYS monotherapy.

Conclusions regarding comparative efficacy of PEGASYS and lamivudine treatment based upon the end of follow-up results are limited by the different mechanisms of action of the two compounds. Most treatment effects of lamivudine are unlikely to persist 24 weeks after therapy is withdrawn.

Pediatric Patients

Study 10 was conducted in previously untreated pediatric subjects aged 3 to less than 18 years (51% < 12 years old) with HBeAg-positive CHB in the immune-active phase. Subjects with cirrhosis were not enrolled in this study. A total of 151 subjects without advanced fibrosis were randomized 2:1 to PEGASYS (group A, n=101) or untreated control (group B, n=50), respectively. Subjects with advanced fibrosis were assigned to PEGASYS treatment (group C, n=10). Subjects in groups A and C (n=111) were treated with PEGASYS once weekly for 48 weeks according to dosing regimen based on body surface area, whereas subjects in group B were observed for a period of 48 weeks (principal observation period). Subjects in group B had the choice to switch to treatment with PEGASYS after Week 48 of the principal observation period. All subjects were followed up for 24 weeks post-treatment (groups A and C), or post-principal observation period (group B). Response rates in groups A and B at the end of 24 weeks follow-up are presented in Table 16. Efficacy response in group C to PEGASYS treatment was similar to that seen in group A.

Table 16 Serological, Virological and Biochemical Responses in Pediatric Subjects with Chronic Hepatitis B
Endpoints [Endpoints measured after 48 weeks treatment with PEGASYS or observation and 24 weeks follow-up.] | Group A (PEGASYS treatment) (N=101) | Group B (Untreated) [Subjects switched to PEGASYS treatment post-principal observation period and before Week 24 follow-up were counted as non-responders.] (N=50)
HBeAg Seroconversion | 26% [Odds Ratio (95% CI) Group A vs Group B = 5.43 (1.54 - 19.20);] | 6.0%
HBV DNA < 20,000 IU/mL [Similar to endpoint of HBV DNA < 10 5 copies/mL. COBAS AMPLICOR HBV MONITOR: HBV-DNA (IU/mL) = HBV-DNA (copies/mL) / 5.26)] | 34% | 4.0%
HBV DNA < 2,000 IU/mL | 29% | 2.0%
ALT Normalization | 52% | 12.0%
HBsAg Seroconversion | 8% | 0.0%
Loss of HBsAg | 9% | 0.0%

16 HOW SUPPLIED/STORAGE AND HANDLING

PEGASYS (peginterferon alfa-2a) injection is a sterile, preservative-free, colorless to slightly yellowish solution administered subcutaneously.

Each PEGASYS Single-Dose Vial Package Contains:
A box containing 180 mcg per 1 mL solution in a single-dose vial. | (NDC 82154-0449-1)

Each PEGASYS Prefilled Syringe Monthly Convenience Pack Contains:
A box containing four 180 mcg per 0.5 mL (½ cc) single-dose prefilled syringes with 4 needles. Each prefilled syringe is supplied with a 27-gauge, ½-inch needle with a needle-stick protection device. | (NDC 82154-0451-4)

Storage and Handling

Store in the refrigerator at 2°C to 8°C (36°F to 46°F). Do not leave PEGASYS out of the refrigerator for more than 24 hours. Do not freeze or shake. Protect from light. Vials and prefilled syringes are for single use only. Discard any unused portion remaining in the vial, prefilled syringe.

Disposal Instructions

If home use is prescribed, a puncture-resistant container for the disposal of used needles and syringes should be supplied to the patients. Patients should be thoroughly instructed in the importance of proper disposal and cautioned against any reuse of any needles and syringes. The full container should be disposed of according to the directions provided by the physician [see FDA-Approved Medication Guide] .

17 PATIENT COUNSELING INFORMATION

- Advise the patient to read the FDA-approved patient labeling (Medication Guideand Instructions for Use)

Patients receiving PEGASYS alone or in combination with an approved HCV antiviral drug should be directed in its appropriate use, informed of the benefits and risks associated with treatment, and referred to FDA-approved patient labeling (Medication Guideand Instructions for Use).

Pregnancy

Patients must be informed that ribavirin must not be used by women who are pregnant or by men whose female partners are pregnant. ribavirin therapy should not be initiated until a report of a negative pregnancy test has been obtained immediately before starting therapy. Female patients of childbearing potential and male patients with female partners of childbearing potential must be advised of the teratogenic/embryocidal risks and must be instructed to practice effective contraception during ribavirin therapy and for 6 months post-therapy. Patients should be advised to notify the healthcare provider immediately in the event of a pregnancy [see Contraindications (4)and Warnings and Precautions (5.1)] .

Women of childbearing potential and men must use two forms of effective contraception during treatment and during the 6 months after treatment has been stopped; routine monthly pregnancy tests must be performed during this time [see Contraindications (4), Warnings and Precautions (5.1), Use in Specific Populations (8.1), and ribavirin prescribing information] .

To monitor maternal and fetal outcomes of pregnant women exposed to ribavirin, the ribavirin Pregnancy Registry has been established. Patients should be encouraged to register by calling 1-800-593-2214.

Flu-like symptoms

Inform patients that flu-like symptoms are very common in patients taking PEGASYS. Symptoms may include tiredness, weakness, fever, chills, muscle aches, joint pain, and headaches. Inform patients that some of these symptoms may be decreased by injecting PEGASYS in the evening. Also inform patients which over-the-counter medicines can be taken to help prevent or decrease some of the symptoms.

Laboratory Evaluations and Hydration

Patients should be advised that laboratory evaluations are required before starting therapy and periodically thereafter [see Warnings and Precautions (5.17)] . Patients should be instructed to remain well hydrated, especially during the initial stages of treatment.

General Information

Patients should be questioned about prior history of drug abuse before initiating PEGASYS; as relapse of drug addiction and drug overdoses have been reported in patients treated with interferons.

Patients should be informed that it is not known if therapy with PEGASYS will prevent transmission of HBV infection to others or prevent cirrhosis, liver failure or liver cancer that might result from HBV infection.

Patients should be informed that the effect of treatment of hepatitis C infection on transmission is not known, and that appropriate precautions to prevent transmission of the hepatitis C virus during treatment or in the event of treatment failure should be taken.

Patients who develop dizziness, confusion, somnolence, and fatigue should be cautioned to avoid driving or operating machinery.

Patients should be advised to avoid drinking alcohol to reduce the chance of further injury to the liver.

Patients should not switch to another brand of interferon without consulting their healthcare provider.

Dosing Instructions

Patients should be advised to take their prescribed dose of PEGASYS on the same day and approximately same time each week. Patients should also be advised that if they miss a dose, but remember within 2 days, to take their missed dose as soon as they remember and then to take their next dose on the day they normally do. If they remember when more than 2 days have passed, patients should be advised to consult their healthcare provider. Patients should also be advised to consult their healthcare provider if the full dose is not received (e.g., leakage around the injection site).

Patients must be instructed on the use of aseptic techniques when administering PEGASYS. Appropriate training for preparation using the vial and prefilled syringe must be given by a healthcare provider, including a careful review of the PEGASYS Medication Guide and Instructions for Use for the vial and prefilled syringe.

Patients should be instructed to allow the vial and prefilled syringe to come to room temperature and for condensation on the outside of the prefilled syringe to disappear before use. The following instructions should be given:

- Vial: warm the refrigerated medicine by gently rolling in the palms of the hands for about one minute.
- Pre-filled syringe: lay the syringe on a flat clean surface and wait a few minutes until it reaches room temperature. If condensation water is observed on the outside of the syringe, wait another few minutes until it disappears.

Patients should be advised not to shake the vial and prefilled syringe as foaming may occur.

Patients should be advised to choose a different place on either the thigh or abdomen each time an injection is made.

Revised: February 2024

PEGASYS® is a registered trademark of pharmaand GmbH

Manufactured by:
pharmaand GmbH
Taborstrasse 1,
1020 Wien
Austria

U.S. License No. 2291

Distributed by:
Summit SD, LLC.
255 Northwest Victoria Drive, Suite A
Lee's Summit, MO 64086

© 2023 pharmaand GmbH, All rights reserved.

Medication Guide
PEGASYS®(PEG-ah-sis)
(peginterferon alfa-2a)
injection, for subcutaneous use

Important: If you are taking PEGASYS with other medicines for treatment of hepatitis C, you should also read the Medication Guides or Patient Information that comes with the other medicines.

What is the most important information I should know about PEGASYS?

Ribavirin in combination with PEGASYS may cause birth defects or death of your unborn baby.If you are pregnant or your sexual partner is pregnant or plans to become pregnant, do not take PEGASYS and ribavirin combination therapy. You or your sexual partner should not become pregnant during treatment with PEGASYS and ribavirin combination therapy and for 6 months after treatment is over. You must use 2 effective forms of birth control, one of which should be a condom with spermicide during treatment with PEGASYS and ribavirin combination therapy, and for the 6 months after the last dose.

- Females must have a pregnancy test before starting PEGASYS and ribavirin combination therapy, every month while being treated, and every month for the 6 months after stopping treatment with PEGASYS and ribavirin combination therapy.
- If you or your female sexual partner becomes pregnant during treatment with PEGASYS and ribavirin or within 6 months after you stop taking PEGASYS and ribavirin,tell your healthcare provider right away. You or your healthcare provider should contact the ribavirin Pregnancy Registry by calling 1-800-593-2214. The ribavirin Pregnancy Registry collects information about the health of you and your baby if you take PEGASYS and ribavirin during pregnancy or if you become pregnant within 6 months after you stop taking PEGASYS and ribavirin.

Mental health problems and suicide. PEGASYS may cause you to develop mood or behavioral problems, including:

- irritability (getting upset easily)
- depression (feeling low, feeling bad about yourself or feeling hopeless) and anxiety
- aggressive behavior
- former drug addicts may fall back into drug addiction or overdose
- thoughts of hurting yourself or others, or suicide

Heart problems.PEGASYS may cause heart problems, including:

- high blood pressure
- fast heart rate or abnormal heart beat
- chest pain

- heart attacks
- trouble breathing

Stroke or symptoms of a stroke.Symptoms may include weakness, loss of coordination, and numbness. Stroke or symptoms of a stroke may happen in people who have some risk factors or no known risk factors for a stroke.

New or worsening autoimmune problems.Some people taking PEGASYS develop autoimmune problems (a condition where the body's immune cells attack other cells or organs in the body), such as rheumatoid arthritis, systemic lupus erythematosus, and psoriasis. In some people who already have an autoimmune problem, it may get worse during your treatment with PEGASYS.

Infections. Symptoms may include:

- fever
- chills
- burning and painful urination

- urinating often
- coughing up yellow or pink mucus (phlegm)

Before and during treatment with PEGASYS you will need to see your healthcare provider regularly and have blood tests to make sure that your treatment is working and to check for side effects.

PEGASYS can cause serious side effects. Some of these side effects may cause death. Tell your healthcare provider right away if you have any of these symptoms during treatment with PEGASYS.

For more information about side effects, see " What are the possible side effects of PEGASYS?"

What is PEGASYS?

PEGASYS is a prescription medicine that is:

- used with other hepatitis C virus (HCV) antiviral medicines to treat adults who have chronic (lasting a long time) hepatitis C infection and compensated liver disease.
- used alone to treat adults with chronic hepatitis C (CHC) and compensated liver disease, and who are not able to take other HCV antiviral medicines.
- used with ribavirin to treat children 5 years of age and older who have CHC and compensated liver disease.

PEGASYS should not be used alone or with ribavirin, without taking other HCV antiviral medicines, to treat people with CHC who have taken interferon-alfa and it did not work.

PEGASYS should not be used to treat people with CHC who have received an organ transplant.

PEGASYS is a prescription medicine that is:

- used alone to treat adults and children 3 years and older with chronic hepatitis B (CHB) virus who show signs that the virus is damaging the liver

It is not known if PEGASYS is safe and effective in:

- children with CHC under 5 years of age or children with CHB under 3 years of age.
- people with Hepatitis B virus (HBV) who also have HCV or HIV infection
- people with HCV who also have HBV, or HIV infection and their CD4+ cell count is less than 100 cells/mm^3

Who should not take PEGASYS?

Do not take PEGASYS if you:

- have had a serious allergic reaction to another alpha-interferon medicine or to any of the ingredients in PEGASYS. Symptoms of a serious allergic reaction to alpha-interferon may include itching, swelling of your face, tongue, throat, trouble breathing, feeling dizzy or faint, and chest pain. See the end of this Medication Guide for a list of the ingredients in PEGASYS.
- have certain types of hepatitis caused by your immune system attacking your liver (autoimmune hepatitis)
- have certain other liver problems

Do notgive PEGASYS to a baby under 1 year of age. PEGASYS contains benzyl alcohol. Benzyl alcohol can cause nervous system problems and other problems which may lead to death.

Do nottake PEGASYS in combination with ribavirin if you:

- are pregnant, or plan to get pregnant during treatment, or during the 6 months after treatment
- are a male with a female sexual partner who is pregnant or plans to become pregnant at any time during treatment with ribavirin or during the 6 months after your treatment has ended.

Talk to your healthcare provider before taking PEGASYS if you have any of these conditions.

Before taking PEGASYS tell your healthcare provider about all of your medical conditions, including if you :

- have or ever had any problems with your heart, including heart attack
- have high blood pressure
- have liver problems (other than hepatitis B or C)
- have lung problems
- have thyroid problems
- have diabetes
- have colitis (inflammation of your intestine)
- have any kind of autoimmune disease (where the body's immune system attacks the body's own cells), such as psoriasis, systemic lupus erythematosus, or rheumatoid arthritis
- have or ever had low blood cell counts
- have cancer
- have or had blood disorders (bleeding problems or a blood clot, thalassemia major or sickle-cell anemia)
- hepatitis B or C infection
- have Human Immunodeficiency Virus -1 (HIV-1) infection
- have kidney problems
- have high blood triglyceride levels (fat in your blood)
- have had an organ transplant
- have ever been addicted to drugs or alcohol
- are being treated for a mental illness or had treatment in the past for any mental illness, including depression and suicidal behavior.
- are pregnant or plan to become pregnant. PEGASYS can harm your unborn baby. Tell your healthcare provider if you become pregnant during treatment with PEGASYS. See “What is the most important information I should know about PEGASYS?” if you take PEGASYS in combination with ribavirin.

Females who are able to become pregnant:

Your healthcare provider should do a pregnancy test before you start treatment with PEGASYS.

You should use effective birth control (contraception) during treatment with PEGASYS.

- are breastfeeding or plan to breastfeed. It is not known if PEGASYS passes into your breast milk. You and your healthcare provider should decide if you will use PEGASYS or breastfeed. You should not do both.
  - If you have HIV-1 infection and are being treated with PEGASYS, you should not breastfeed because of the risk of passing HIV-1 to your baby.

Tell your healthcare provider about all the medicines you take,including prescription and over-the-counter medicines, vitamins and herbal supplements. PEGASYS and certain other medicines may affect each other and cause side effects.

- Especially tell your healthcare provider if you take:

- telbivudine
  - theophylline. Your healthcare provider may need to monitor the amount of theophylline in your body and make changes to your theophylline dose.
  - any HIV-1 medicines
  - methadone hydrochloride

- Keep a list of your medicines and show it to your healthcare provider and pharmacist when you get a new medicine.
- Do not start a new medicine without telling your healthcare provider. Your healthcare provider can tell you if it is safe to take PEGASYS with other medicines.

How should I take PEGASYS?

- PEGASYS is given by injection under the skin (subcutaneous injection).
- Your healthcare provider will decide on your dose of PEGASYS and when you will take it. PEGASYS is usually injected 1 time each week. For children 3 years of age and older infected with hepatitis B virus or 5 years of age and older infected with hepatitis C virus, your healthcare provider will prescribe the dose of PEGASYS based on your child's height and weight.
- If your healthcare provider decides that you or a caregiver can inject PEGASYS, inject it exactly as prescribed.
- See the Instructions for Usethat comes with your PEGASYS for detailed instructions about how to prepare and inject a dose of PEGASYS.
- Your healthcare provider may decrease your dose, temporarily stop, or permanently stop your treatment with PEGASYS if you develop certain side effects. Do not change your dose unless your healthcare provider tells you to change it.
- Do not switch to another brand of interferon without talking to your healthcare provider.
- Take your prescribed dose of PEGASYS 1 time each week, on the same day of each week and at approximately the same time.
- Do not take more than your prescribed dose.
- PEGASYS comes as a liquid:
  - in a single-dose vial
  - in a single-dose prefilled syringe
    Your healthcare provider will decide which one is best for you.
- Your healthcare provider should show you how to prepare and measure, and injectyour dose of PEGASYS before you use the single-dose vial or single-dose prefilled syringe for the first time.
- When you get your prescription from the pharmacy, ask your pharmacist for the syringe and needle that you need to use to prepare and inject a dose of PEGASYS from the single-dose vial.
- If you will be injecting a child with PEGASYS, you will need a special syringe called a tuberculin syringe, which can measure doses of PEGASYS that are 1 milliliter (1mL) or less.
- Do not reuse PEGASYS single-dose vials, single-dose prefilled syringes and needles.
- If you miss your dose:
  - If you remember within 2 days of when you should have taken PEGASYS, give yourself an injection of PEGASYS as soon as you remember. Take your next dose on the day you would usually take it.
  - If more than 2 days have passed, ask your healthcare provider what you should do.
- If you take more than the prescribed amount of PEGASYS, call your healthcare provider right away. Your healthcare provider may want to examine you and do blood tests.

What should I avoid while taking PEGASYS?

- Avoid drinking alcohol. This may make your liver disease worse.
- Avoid driving or operating machinery if you become dizzy, confused, very sleepy, or tired during treatment with PEGASYS.

What are the possible side effects of PEGASYS?

PEGASYS can cause serious side effects including:

- See " What is the most important information I should know about PEGASYS? "
- Blood problems.PEGASYS can affect your bone marrow and cause low red blood cell, low white blood cell and low platelet counts. These blood counts may fall to dangerously low levels. If your blood cell counts become very low, you can get anemia, infections or have problems with bleeding and bruising.
- Thyroid problems. Symptoms of thyroid changes include feeling cold or hot all the time, a change in your weight, and changes to your skin, trouble concentrating.
- Blood sugar problems. PEGASYS may cause low blood sugar (hypoglycemia), high blood sugar (hyperglycemia) or diabetes. If you have high blood sugar or diabetes before starting PEGASYS, talk to your healthcare provider before you take PEGASYS. If you develop high blood sugar or diabetes during treatment with PEGASYS, your healthcare provider may tell you to stop PEGASYS and prescribe a different medicine for you.

Symptoms of low blood sugar may include :

- feeling faint
- headaches,
- sweating

- anxiousness
- confusion
- weakness

Symptoms of high blood sugar or diabetes may include:

- increased thirst
- tiredness
- urinating more often than normal

- increased appetite
- weight loss
- your breath smells like fruit

- Serious eye problems. PEGASYS may cause eye problems that may lead to vision loss or blindness. You should have an eye exam before you start taking PEGASYS. If you have eye problems or have had them in the past, you may need eye exams during treatment with PEGASYS. Tell your healthcare provider or eye doctor right away if you have any vision changes during treatment with PEGASYS.
- Serious liver problems,worsening of liver problems including liver failure and death. Symptoms may include:

- nausea
- loss of appetite
- tiredness
- diarrhea
- yellowing of your skin or the white part of your eyes

- bleeding more easily than normal
- swelling of your stomach area (abdomen)
- confusion
- sleepiness
- you cannot be awakened (coma)

- Lung problems, including:

- trouble breathing
- pneumonia
- inflammation of lung tissue

- new or worse high blood pressure of the lungs (pulmonary hypertension). This can be severe and may lead to death.

You may need to have a chest X-ray or other tests if you develop fever, cough, shortness of breath or other symptoms of a lung problem during treatment with PEGASYS.

- Inflammation of your intestines (colitis). Symptoms of inflammation of your intestines (colitis) may include:

- severe stomach area (abdomen) pain
- fever

- bloody diarrhea or blood bowel movements

- Inflammation of your pancreas (pancreatitis). Symptoms of inflammation of your pancreas (pancreatitis) may include:

- severe stomach (abdomen) pain
- severe back pain
- nausea

- vomiting
- fever

- Serious allergic reactions and skin reactions. Get medical help right away if you get any of the following symptoms:

- itching
- swelling of your face, eyes, lips, tongue, or throat
- trouble breathing
- skin rash, hives, sores in your mouth, or your skin blisters and peels

- chest pain
- feeling faint

- Effect on growth in children. A delay in height increase or weight gain has happened in children with CHC during
  treatment with PEGASYS and ribavirin, and in children with CHB during treatment with PEGASYS. Some children
  may not reach the height and weight they were expected to have before treatment after they stop treatment with
  PEGASYS. Talk to your healthcare provider if you are concerned about your child’s growth during treatment or after
  stopping treatment with PEGASYS. Talk to your healthcare provider if you are concerned about your child's growth during treatment with PEGASYS.
- Nerve problems. People who take PEGASYS or other alfa interferon products with telbivudine (Tyzeka) for hepatitis B can develop nerve problems such as continuing numbness, tingling, or burning sensation in the arms or legs (peripheral neuropathy). Call your healthcare provider if you have any of these symptoms.

Tell your healthcare provider right away if you have any of the symptoms listed above.

The most common side effects of PEGASYS include:

- flu-like symptoms. Symptoms may include tiredness, weakness, fever, chills, muscle aches, joint pain, and headaches. Some of these symptoms may be decreased by injecting your PEGASYS dose in the evening. Talk to your healthcare provider about which over-the-counter medicines you can take to help prevent or decrease some of the symptoms.

Tell your healthcare provider if you have any side effect that bothers you or that does not go away.

These are not all of the side effects of PEGASYS.

Call your doctor for medical advice about side effects. You may report side effects to FDA at 1-800-FDA-1088.

You may also report side effects to pharma& agent at 1-888-814-7734.

How should I store PEGASYS?

- Store PEGASYS single-dose vials and single-dose prefilled syringes in a refrigerator at 36°F to 46°F (2°C to 8°C).
- Do notleave PEGASYS out of the refrigerator for more than 24 hours.
- Do notfreeze or shake PEGASYS.
- Protect PEGASYS from light.

Keep PEGASYS and all medicines out of the reach of children.

General information about the safe and effective use of PEGASYS.

Medicines are sometimes prescribed for purposes other than those listed in a Medication Guide. Do not use PEGASYS for a condition for which it was not prescribed. Do not give PEGASYS to other people, even if they have the same symptoms that you have. It may harm them. You can ask your healthcare provider or pharmacist for information that is written for health professionals.

What are the ingredients in PEGASYS?

Active ingredient: interferon alfa-2a

Inactive ingredients: acetic acid, benzyl alcohol, polysorbate 80, sodium acetate trihydrate, and sodium chloride.

Manufactured by: pharmaand GmbH, Taborstrasse 1, 1020, Wien. Austria

U.S. License No. 2291
Distributed by: Summit SD, LLC, 255 Northwest Victoria Drive, Suite A, Lee’s Summit, MO 64086
PEGASYS® is a registered trademark of pharmaand GmbH

This Medication Guide has been approved by the U.S. Food and Drug Administration

Revised: February 2024

Instructions for Use PEGASYS®(PEG-ah-sis) (peginterferon alfa-2a) Injection For Subcutaneous Use Prefilled Syringe

First read the Medication Guide that comes with PEGASYS for the most important information you need to know about PEGASYS. Be sure that you read, understand and follow these Instructions for Use before injecting PEGASYS. Your healthcare provider should show you how to prepare, measure and inject PEGASYS properly before you use it for the first time. Ask your healthcare provider if you have any questions.

PEGASYS prefilled syringes come in a Monthly Convenience Pack that contains 4 prefilled syringes of PEGASYS in a box with 4 needles. Each needle has a needle-stick protection device.

Before starting, collect all of the supplies that you will need to use for preparing and injecting PEGASYS. You will need the following supplies:

- 1 single-dose disposable prefilled syringe of PEGASYS
- 1 needle with needle-stick protection device
- several alcohol pads
- You will also need a puncture-resistant disposable container to throw away used prefilled syringes and needles as soon as you finish your injection. See " How should I dispose of used syringes and needles?"

Important:

- Never reuse disposable prefilled syringes and needles.
- Throw away the prefilled syringe of PEGASYS after you use it 1 time, even if there is any medicine left in it.
- Do notshake PEGASYS. If shaken, PEGASYS may not work properly.

How should I prepare a dose of PEGASYS?

1. Find a well-lit, clean, flat surface such as a table.
2. Take a carton containing PEGASYS out of the refrigerator. Check the date on the carton the PEGASYS comes in. Make sure the expiration date has not passed. Do not use if the expiration date has passed (see Figure A).
3. Figure A:
5. Remove the prefilled syringe of PEGASYS from the carton. Look at the prefilled syringe of PEGASYS. The solution should be clear and colorless to slightly yellowish, without particles (see Figure B). If there is foam in the solution, put it back in the refrigerator for use at a later time and use another syringe.
6. Figure B:
8. Do notuse the prefilled syringe of PEGASYS if:
  1. the medicine remains cloudy after a few minutes at room temperature
  2. has particles
  3. the medicine is not colorless to slightly yellowish
  4. the expiration date has passed (see Figure C).
9. Figure C:
11. Wash your hands well with soap and warm water. Keep your work area, your hands, and injection site clean to decrease the risk of infection.
12. Lay the syringe on a flat clean surface and wait a few minutes until it reaches room temperature. If you notice condensation water on the outside of the syringe, wait another few minutes until it disappears.

How do I attach the needle to the PEGASYS prefilled syringe?

- Remove the needle from its package. Do notremove the needle shield yet. Keep the needle covered until just before you give the injection (see Figure D).
- Figure D:
- Remove and throw away the rubber cap from the tip of the syringe barrel (see Figure E).
- Figure E:
- With one hand, hold the syringe by the barrel. With your other hand, hold the needle close to the hub where the green needle cover connects to the syringe (see Figure F).
- Figure F:
- Push the needle onto the syringe and tighten by using an easy twisting motion in the direction of the arrow (see Figure G).
- Figure G:
- Here is a picture of what the syringe will look like after you finish attaching the needle (see Figure H).
- Figure H:
- Lay the syringe and needle down on your clean work surface. Be sure that the plastic needle shield covers the needle. Never let the needle touch any surface.

How should I choose a site for injection?

- You can inject PEGASYS under the skin on your stomach or thigh (see Figure I). Avoid your navel and waistline. You should use a different place each time you give yourself an injection.
- Figure I:
- Clean the area using an alcohol pad. Let the skin air dry.

How do I prepare the PEGASYS prefilled syringe for injection?

- Pull the green needle cover back from the needle toward the syringe barrel. The green needle cover will stay in the position you set. Do not remove it. This is the needle-stick protection device (see Figure J).
- Figure J:
- Hold the syringe and needle tightly at the hub. Gently rock the plastic needle shield back and forth to prepare for removal. Remove the plastic needle shield by pulling it straight off (see Figure K).
- Figure K:
- Remove air bubbles from the syringe.
  - Hold the syringe with the needle pointing up to the ceiling.
  - Using your thumb and finger, gently tap the syringe to bring air bubbles to the top (see Figure L).
  - Press the plunger in slightly to push air bubbles out of the syringe.
  - Figure L:
- Depending on the dose of PEGASYS that your healthcare provider prescribes, you may have to get rid of (discard) some of the medicine from the prefilled syringe before you inject the medicine. The syringe has markings for 180 mcg, 135 mcg, and 90 mcg. Your healthcare provider will tell you which mark to use (see Figure Mand Figure N).

1. Figure M:

1. Figure N:

1. Do notdecrease or increase your dose of PEGASYS unless your healthcare provider tells you to.

How do I give the injection of PEGASYS?

- Position the point of the needle (the bevel) so it is facing up (see Figure O).
- Figure O:
- Pinch a fold of skin on your stomach or thigh firmly with your thumb and forefinger (see Figure P).
- Figure P:
- Hold the syringe like a pencil at a 45° to 90° angle to your skin. With a quick "dart-like" motion, push the needle into the skin as far as it will go (see Figure Q).
- Figure Q:
- After the needle is inserted, remove the hand used to pinch the skin and use it to hold the syringe barrel.
  - Pull the plunger of the syringe back slightly.
  - If blood comes into the syringe,the needle has entered a blood vessel.
    - Do not inject PEGASYS. Withdraw the needle and throw away the syringe and needle in the puncture-resistant container. See “ How should I dispose of used syringes and needles?”
    - Then, repeat steps 1 through 16 with a new prefilled syringe and prepare a new injection site.
  - If no blood is present in the syringe,inject the medicine by gently pressing the plunger all the way down the syringe barrel, until the syringe is empty.
- When the syringe is empty, pull the needle out of the skin. Wipe the area with an alcohol pad.
- To prevent needle-stick injuries, before you dispose of the syringe and needle, push the green needle cover toward the needle (see Figure R). Then place the free end of the green cap on a flat surface and push down with a firm and quick motion until it clicks and covers over the needle (see Figure S).

1. Figure R:

1. Figure S:

- Throw away the used syringe and needle right away as described below. See “ How should I dispose of used syringes and needles?”

How should I dispose of used syringes and needles?

- Put your used needles and syringes in a FDA-cleared sharps disposal container right away after use. Do not throw away (dispose of) loose needles and syringes in your household trash.
- If you do not have a FDA-cleared sharps disposal container, you may use a household container that is:
  - made of a heavy-duty plastic,
  - can be closed with a tight-fitting, puncture-resistant lid, without sharps being able to come out,
  - upright and stable during use,
  - leak-resistant, and
  - properly labeled to warn of hazardous waste inside the container.
- When your sharps disposal container is almost full, you will need to follow your community guidelines for the right way to dispose of your sharps disposal container. There may be state or local laws about how you should throw away used needles and syringes. For more information about safe sharps disposal, and for specific information about sharps disposal in the state that you live in, go to the FDA's website at: http://www.fda.gov/safesharpsdisposal.
- Do not dispose of your used sharps disposal container in your household trash unless your community guidelines permit this. Do not recycle your used sharps disposal container.

Always keep the puncture-resistant container out of the reach of children.

How should I store PEGASYS?

- Store PEGASYS prefilled syringes in a refrigerator at 36°F to 46°F (2°C to 8°C).
- Do not leave PEGASYS out of the refrigerator for more than 24 hours.
- Do not freeze or shake PEGASYS.
- Protect PEGASYS from light.

This Instructions for Use has been approved by the U.S. Food and Drug Administration.

Revised: Februaury 2024

PEGASYS® is a registered trademark of pharmaand GmbH

Manufactured by:

pharmaand GmbH

Taborstrasse 1,
1020 Wien
Austria

U.S. License No. 2291

Distributed by:

Summit SD, LLC.

255 Northwest Victoria Drive, Suite A
Lee’s Summit, MO 64086

© 2023 pharmaand GmbH, All rights reserved.

Instructions for Use PEGASYS®(PEG-ah-sis) (peginterferon alfa-2a) Injection For Subcutaneous Use Vial

First read the Medication Guide that comes with PEGASYS for the most important information you need to know about PEGASYS. Be sure that you read, understand and follow these Instructions for Use before injecting PEGASYS. Your healthcare provider should show you how to prepare, measure, and inject PEGASYS properly before you use it for the first time. Ask your healthcare provider if you have any questions.

Before starting, collect all of the supplies that you will need to use for preparing and injecting PEGASYS. You will need the following supplies:

- 1 vial of PEGASYS
- 1 single-use disposable syringe and needle
- several alcohol pads
- You will also need a puncture-resistant disposable container to throw away used syringes, needles, and vials as soon as you finish your injection. See “ How should I dispose of used syringes, needles, and vials?”

Follow your healthcare provider's instructions for the type of syringe and needle to use to prepare and inject your dose. If you will be injecting a child with PEGASYS, you will need a special syringe called a tuberculin syringe, which can measure doses of PEGASYS that are 1 milliliter (1mL) or less. When you get your prescription from the pharmacy, ask your pharmacist for the syringe and needle that you need to prepare and inject a dose of PEGASYS from the single-dose vial.

Important:

- Never reuse disposable syringes and needles.
- Throw away the vial of PEGASYS after you use it 1 time even if there is medicine left in the vial.
- Do not shake PEGASYS. If shaken, PEGASYS may not work properly.

How should I prepare a dose of PEGASYS?

- Find a well-lit, clean, flat working surface such as a table.
- Take a carton containing PEGASYS out of the refrigerator. Check the date on the carton the PEGASYS comes in. Make sure the expiration date has not passed. Do not use if the expiration date has passed (see Figure A).
- Figure A:
- Wash your hands well with soap and warm water. Keep your work area, your hands, and injection site clean to decrease the risk of infection.
- Remove the vial of PEGASYS from the carton. Look at the vial of PEGASYS. The solution should be clear and colorless to slightly yellowish, without particles (see Figure B).
- Figure B:
- Do not use the vial of PEGASYS if:
  1. the medicine is cloudy
  2. has particles
  3. the medicine is not colorless to slightly yellowish
  4. the expiration date has passed (see Figure B)
- Warm the refrigerated medicine by gently rolling it in the palms of your hands for about one minute. Do not shake PEGASYS.
- Remove (flip off) the plastic cap from the top of the PEGASYS vial (see Figure C). Clean the rubber stopper on the top of the vial with an alcohol pad (see Figure D).

1. Figure C:

1. Figure D:

- If you are not sure how much medicine to use or which mark on the syringe to use, stop and call your healthcare provider right away.

- Open the package for the syringe you are using and if it does not have a needle attached, then attach a new needle to the syringe.
- Remove the protective cap from the needle on the syringe. Never let the needle touch any surface. Fill the syringe with air by pulling back on the plunger to the mark on the syringe barrel that matches the dose prescribed by your healthcare provider (see Figure E).
- Figure E:
- Hold the vial of PEGASYS on your flat surface. Do not touch the cleaned rubber stopper.
- Push the needle straight down through the middle of the rubber stopper on the vial. Slowly inject all the air from the syringe into the air space above the solution. Do not inject air into the fluid (see Figure F).
- Figure F:
- Keep the needle in the vial. Turn the vial upside down.
- Make sure the tip of the needle is in the PEGASYS solution.
- Slowly pull the plunger back to fill the syringe with PEGASYS solution to the dose (mL or cc markings on the syringe) that matches the dose prescribed by your healthcare provider (see Figure G).
- Figure G:
- Do not remove the needle from the vial. Lay the vial and syringe on its side on your flat work surface until you are ready to inject the PEGASYS solution (see Figure H).
- Figure H:

How should I choose a site for injection?

- You can inject PEGASYS under the skin on your stomach or thigh (see Figure I). Avoid your navel and waistline. You should use a different place each time you give yourself an injection.
- Figure I:
- Clean the area using an alcohol pad and let the skin air dry.

How should I give an injection?

- Pick up the vial and syringe from your flat work surface. Remove the syringe and needle from the vial.
  - Hold the syringe in the hand that you will use to inject PEGASYS.
  - Do not touch the needle or allow it to touch the work surface.
- Remove air bubbles from the syringe.
  - Hold the syringe with the needle pointing up to the ceiling.
  - Using your thumb and finger, tap the syringe to bring air bubbles to the top (see Figure J).
  - Press the plunger in slightly to push air bubbles out of the syringe.
  - Figure J:
- Position the point of the needle (the bevel) so it is facing up (see Figure K).
- Figure K:
- Pinch a fold of skin on your stomach or thigh firmly between your thumb and forefinger (see Figure L).
- Figure L:
- Hold the syringe like a pencil at a 45° to 90° angle to your skin. With a quick "dart-like" motion, push the needle into the skin as far as it will go (see Figure M).
- Figure M:
- After the needle is inserted, remove the hand used to pinch the skin and use it to hold the syringe barrel.
  - Pull the plunger of the syringe back slightly.
  - If blood comes into the syringe,the needle has entered a blood vessel.
    - Do not inject PEGASYS. Withdraw the needle and throw away the syringe, needle, and vial in the puncture-resistant container. See “ How should I dispose of used syringes, needles, and vials?”
    - Then, repeat steps 1 through 19 with a new vial of PEGASYS and inject the medicine at a new injection site.
  - If no blood is present in the syringe,inject the medicine by gently pressing the plunger all the way down the syringe barrel, until the syringe is empty.
- When the syringe is empty, pull the needle out of the skin. Wipe the area with an alcohol pad.
- Throw away the used syringe, needle, and vial. See “ How should I dispose of used syringes, needles, and vials?”

How should I dispose of used syringes, needles, and vials?

- Put your used needles and syringes in a FDA-cleared sharps disposal container right away after use. Do not throw away (dispose of) loose needles and syringes in your household trash.
- If you do not have a FDA-cleared sharps disposal container, you may use a household container that is:
  - made of a heavy-duty plastic,
  - can be closed with a tight-fitting, puncture-resistant lid, without sharps being able to come out,
  - upright and stable during use,
  - leak-resistant, and
  - properly labeled to warn of hazardous waste inside the container.
- When your sharps disposal container is almost full, you will need to follow your community guidelines for the right way to dispose of your sharps disposal container. There may be state or local laws about how you should throw away used needles and syringes. For more information about safe sharps disposal, and for specific information about sharps disposal in the state that you live in, go to the FDA's website at: http://www.fda.gov/safesharpsdisposal.
- Do not dispose of your used sharps disposal container in your household trash unless your community guidelines permit this. Do not recycle your used sharps disposal container.

How should I store PEGASYS?

- Store PEGASYS single-dose vials in a refrigerator at 36°F to 46°F (2°C to 8°C).
- Do not leave PEGASYS out of the refrigerator for more than 24 hours.
- Do not freeze or shake PEGASYS.
- Protect PEGASYS from light.

This Instructions for Use has been approved by the U.S. Food and Drug Administration.

Revised: February 2024

PEGASYS® is a registered trademark of pharmaand GmbH

Manufactured by:
pharmaand GmbH
Taborstrasse 1,
1020 Wien
Austria
U.S. License No. 2291

Distributed by:
Summit SD, LLC.
255 Northwest Victoria Drive, Suite A
Lee's Summit, MO 64086

© 2023 pharmaand GmbH, All rights reserved.

PRINCIPAL DISPLAY PANEL - 180 mcg/1 mL Vial Box

NDC 82154-0449-1

Pegasys®
(peginterferon alfa-2a)

180 mcg/1 mL

For Subcutaneous Use
For Single Use
Sterile

ATTENTION PHARMACIST:
Each patient is required to
receive the enclosed
Medication Guide.

Refrigerate Immediately

Vial contains: 180 mcg/1 mL

Rx only

PRINCIPAL DISPLAY PANEL - 180 mcg/0.5 mL Syringe Box

NDC 82154-0451-4

ATTENTION PHARMACIST:
Each patient is required to receive the enclosed
Medication Guide.

Refrigerate Immediately

Pegasys®
(peginterferon alfa-2a)

Rx only

180 mcg/0.5 mL

For Subcutaneous Injection Only
Sterile
Prefilled Syringes Monthly Convenience Pack Package Contains:
4 Single-Use Prefilled Syringes Pegasys®180 mcg/0.5 mL, NDC 82154-0451-1
4 Needles (27-gauge, 1/2-inch)

Each Prefilled Syringe Contains:
180 mcg/0.5 mL